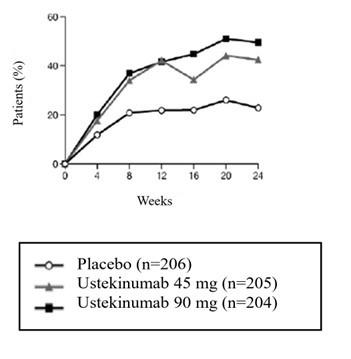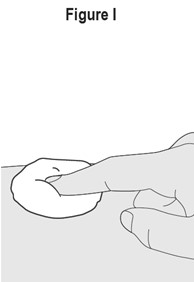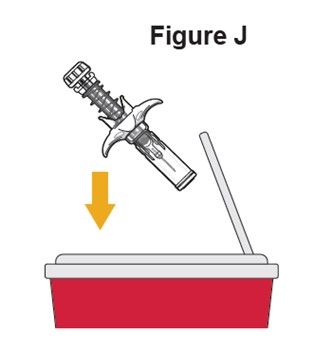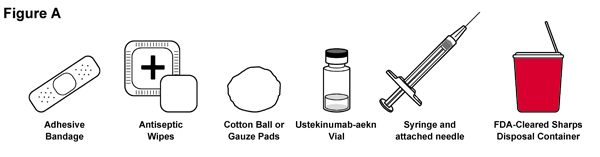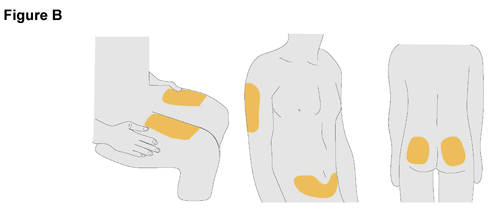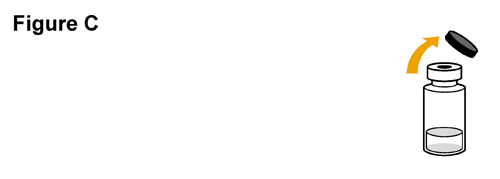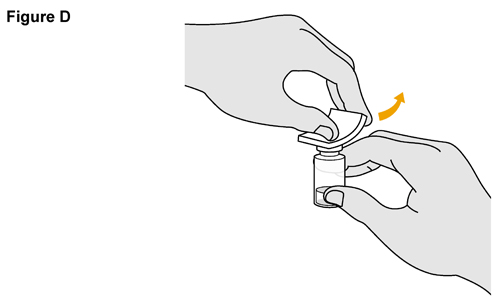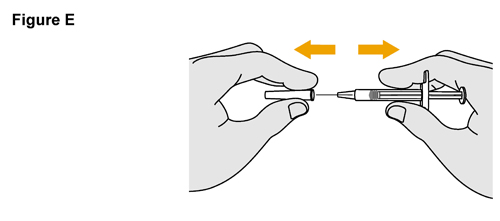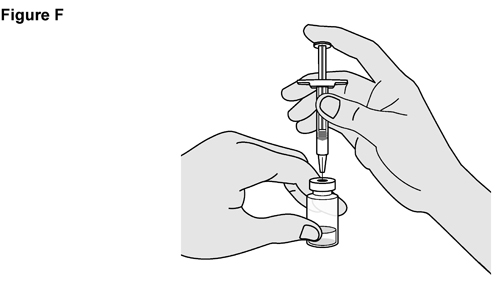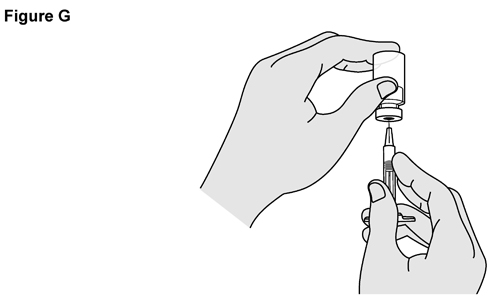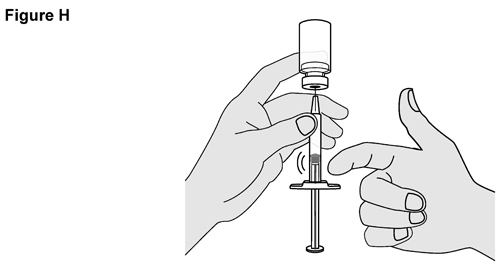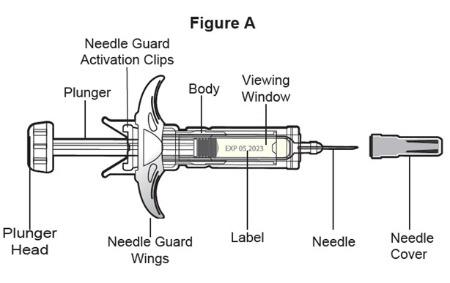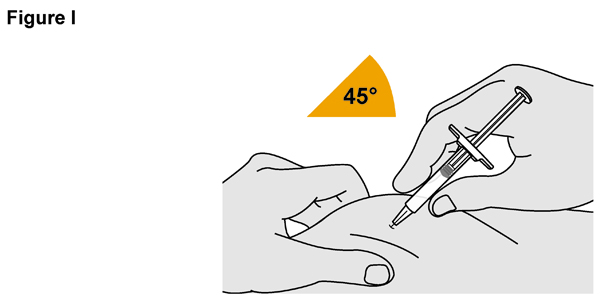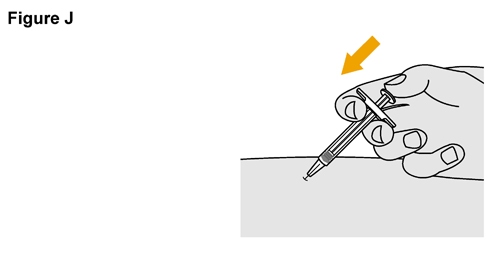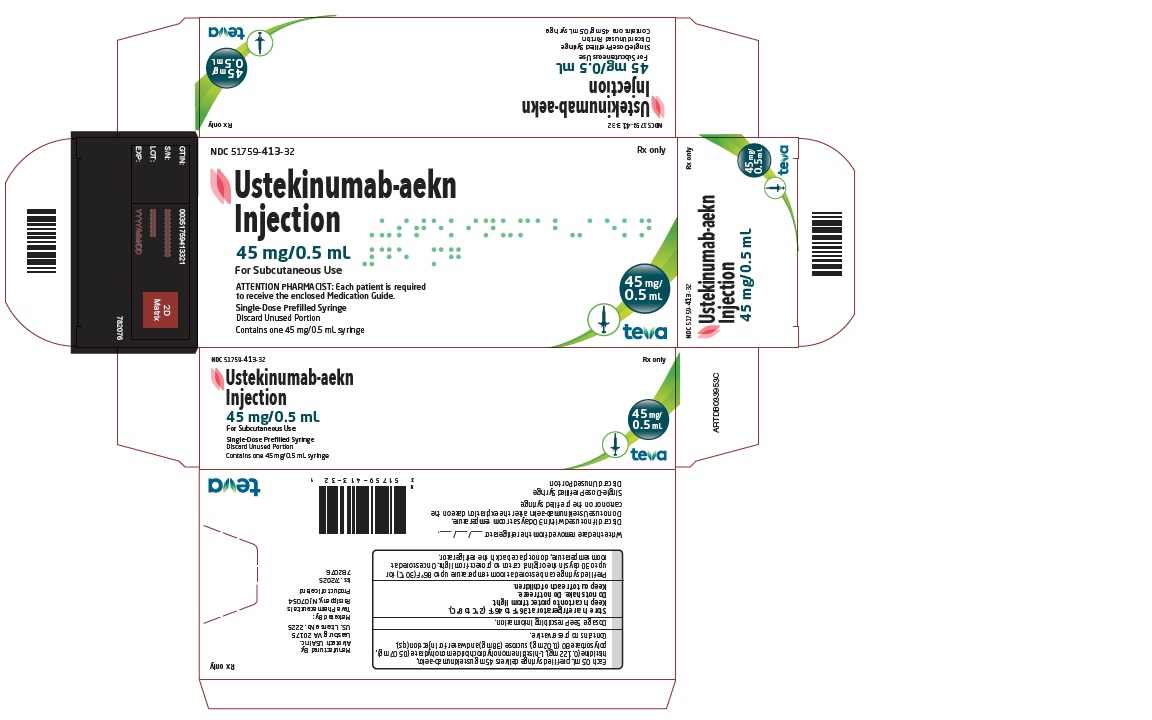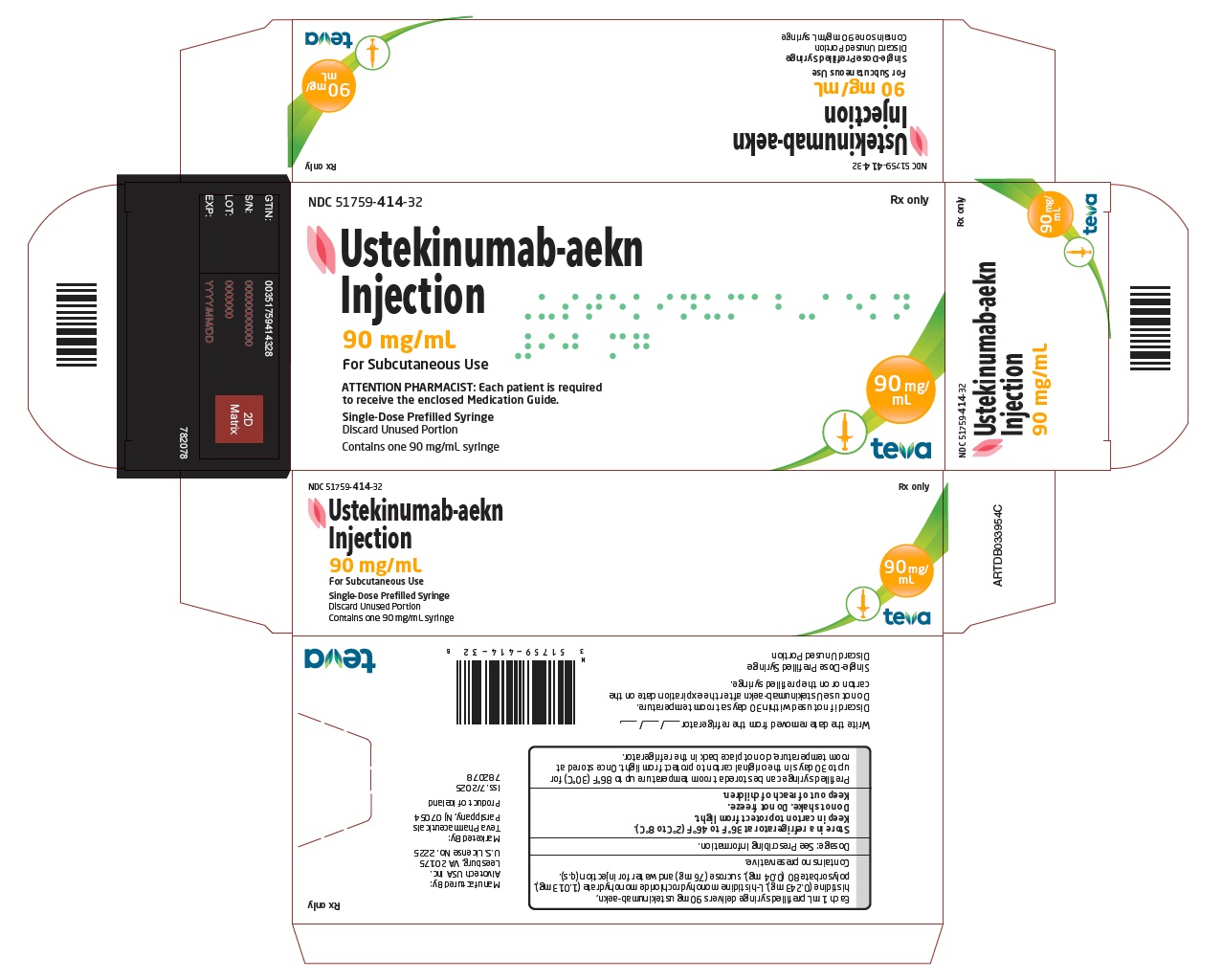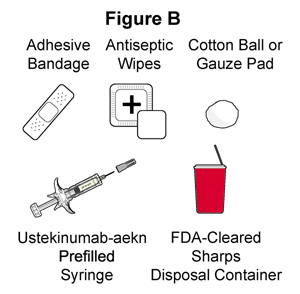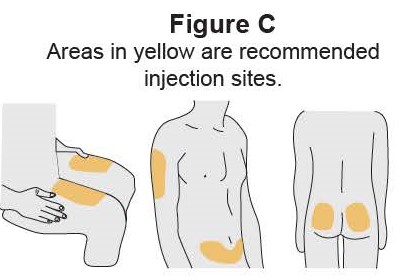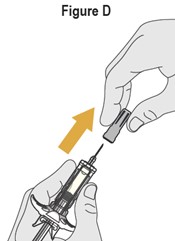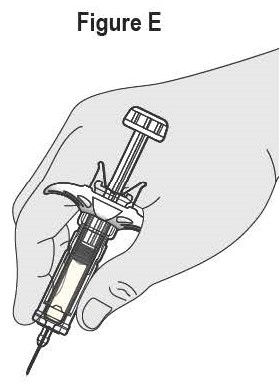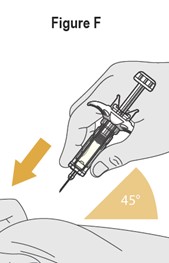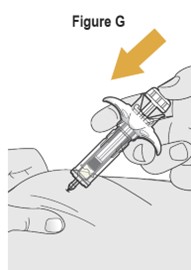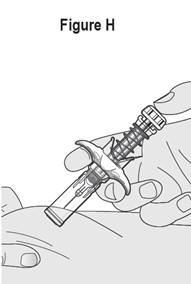 DRUG LABEL: Ustekinumab-aekn
NDC: 51759-413 | Form: INJECTION, SOLUTION
Manufacturer: Teva Pharmaceuticals USA, Inc.
Category: prescription | Type: HUMAN PRESCRIPTION DRUG LABEL
Date: 20260225

ACTIVE INGREDIENTS: USTEKINUMAB-AEKN 45 mg/0.5 mL
INACTIVE INGREDIENTS: HISTIDINE; HISTIDINE MONOHYDROCHLORIDE MONOHYDRATE; POLYSORBATE 80; SUCROSE; WATER

HIGHLIGHTS OF PRESCRIBING INFORMATION

These highlights do not include all the information needed to use USTEKINUMAB-AEKN safely and effectively. See full prescribing information for USTEKINUMAB-AEKN.
USTEKINUMAB-AEKN injection, for subcutaneous or intravenous use
Initial U.S. Approval: 2024
Ustekinumab-aekn is biosimilar [Biosimilar means that the biological product is approved based on data demonstrating that it is highly similar to an FDA-approved biological product, known as a reference product, and that there are no clinically meaningful differences between the biosimilar product and the reference product. Biosimilarity of Ustekinumab-aekn has been demonstrated for the condition(s) of use (e.g., indication(s), dosing regimen(s)), strength(s), dosage form(s), and route(s) of administration described in its Full Prescribing Information.] to STELARA® (ustekinumab).

RECENT MAJOR CHANGES

Dosage and Administration (2.1, 2.2, 2.4) 02/2025
Warnings and Precautions (5.5) 12/2025

1 INDICATIONS AND USAGE

Ustekinumab-aekn is a human interleukin-12 and -23 antagonist indicated for the treatment of:

Adult patients with:

- moderate to severe plaque psoriasis (PsO) who are candidates for phototherapy or systemic therapy. (1.1)
- active psoriatic arthritis (PsA). (1.2)
- moderately to severely active Crohn’s disease (CD). (1.3)
- moderately to severely active ulcerative colitis. (1.4)

Pediatric patients 6 years and older with:

- moderate to severe plaque psoriasis (PsO), who are candidates for phototherapy or systemic therapy. (1.1)
- active psoriatic arthritis (PsA). (1.2)

2 DOSAGE AND ADMINISTRATION

Adult Patients with Plaque Psoriasis Subcutaneous Recommended Dosage (2.1):

Weight Range (kilograms) | Dosage
less than or equal to 100 kg | 45 mg administered subcutaneously initially and 4 weeks later, followed by; 45 mg administered subcutaneously every 12 weeks
greater than 100 kg | 90 mg administered subcutaneously initially and 4 weeks later, followed by; 90 mg administered subcutaneously every 12 weeks

Pediatric Patients 6 Years of Age and Older with Plaque Psoriasis Subcutaneous Recommended Dosage (2.1):

Weight-based dosing is recommended at the initial dose, 4 weeks later, then every 12 weeks thereafter.

Weight Range (kilograms) | Dose
less than 60 kg | 0.75 mg/kg
60 kg to 100 kg | 45 mg
greater than 100 kg | 90 mg

Psoriatic Arthritis Adult Subcutaneous Recommended Dosage (2.2):

- The recommended dosage is 45 mg administered subcutaneously initially and 4 weeks later, followed by 45 mg administered subcutaneously every 12 weeks.
- For patients with co-existent moderate-to-severe plaque psoriasis weighing greater than 100 kg, the recommended dosage is 90 mg administered subcutaneously initially and 4 weeks later, followed by 90 mg administered subcutaneously every 12 weeks.

Psoriatic Arthritis Pediatric 6 years of Age and Older Subcutaneous Recommended Dosage (2.2):

Weight-based dosing is recommended at the initial dose, 4 weeks later, then every 12 weeks thereafter.

Weight Range (kilograms) | Dose
less than 60 kg | 0.75 mg/kg
60 kg or more | 45 mg
greater than 100 kg with co- existent moderate-to-severe plaque psoriasis | 90 mg

Crohn’s Disease and Ulcerative Colitis Initial Adult Intravenous

Recommended Dosage (2.3): A single intravenous infusion using weight-based dosing:

Weight Range (kilograms) | Recommended Dose
up to 55 kg | 260 mg (2 vials)
greater than 55 kg to 85 kg | 390 mg (3 vials)
greater than 85 kg | 520 mg (4 vials)

Crohn’s Disease and Ulcerative Colitis Maintenance Adult Subcutaneous Recommended Dose (2.3):

A subcutaneous 90 mg dose 8 weeks after the initial intravenous dose, then every 8 weeks thereafter.

3 DOSAGE FORMS AND STRENGTHS

Subcutaneous Injection (3)

- Injection: 45 mg/0.5 mL or 90 mg/mL solution in a single-dose prefilled syringe
- Injection: 45 mg/0.5 mL solution in a single-dose vial

Intravenous Infusion (3)

- Injection: 130 mg/26 mL (5 mg/mL) solution in a single-dose vial (3)

4 CONTRAINDICATIONS

Clinically significant hypersensitivity to ustekinumab products or to any of the excipients in Ustekinumab-aekn. (4)

5 WARNINGS AND PRECAUTIONS

- Infections: Serious infections have occurred. Avoid starting Ustekinumab-aekn during any clinically important active infection. If a serious infection or clinically significant infection develops, discontinue Ustekinumab-aekn until the infection resolves. (5.1)
- Theoretical Risk for Particular Infections: Serious infections from mycobacteria, salmonella, and Bacillus Calmette-Guerin (BCG) vaccinations have been reported in patients genetically deficient in IL-12/IL-23. Consider diagnostic tests for these infections as dictated by clinical circumstances. (5.2)
- Tuberculosis (TB): Evaluate patients for TB prior to initiating treatment with Ustekinumab-aekn. Initiate treatment of latent TB before administering Ustekinumab-aekn. (5.3)
- Malignancies: Ustekinumab products may increase risk of malignancy. The safety of ustekinumab products in patients with a history of or a known malignancy has not been evaluated. (5.4)
- Serious Hypersensitivity Reactions: If a severe or other clinically significant hypersensitivity reaction occurs discontinue Ustekinumab-aekn immediately and initiate appropriate medical treatment. (5.5)
- Posterior Reversible Encephalopathy Syndrome (PRES): If PRES is suspected, treat promptly, and discontinue Ustekinumab-aekn. (5.6)
- Immunizations: Avoid use of live vaccines in patients during treatment with Ustekinumab-aekn. (5.7)
- Noninfectious Pneumonia: Cases of interstitial pneumonia, eosinophilic pneumonia, and cryptogenic organizing pneumonia have been reported during post-approval use of ustekinumab products. If diagnosis is confirmed, discontinue Ustekinumab-aekn and institute appropriate treatment. (5.8)

6 ADVERSE REACTIONS

Most common adverse reactions are:

- Psoriasis and Psoriatic Arthritis (≥3%): nasopharyngitis, upper respiratory tract infection, headache, and fatigue. (6.1)
- Crohn’s Disease, induction (≥3%): vomiting. (6.1)
- Crohn’s Disease, maintenance (≥3%): nasopharyngitis, injection site erythema, vulvovaginal candidiasis/mycotic infection, bronchitis, pruritus, urinary tract infection, and sinusitis. (6.1)
- Ulcerative colitis, induction (≥3%): nasopharyngitis (6.1)
- Ulcerative colitis, maintenance (≥3%): nasopharyngitis, headache, abdominal pain, influenza, fever, diarrhea, sinusitis, fatigue, and nausea (6.1)

To report SUSPECTED ADVERSE REACTIONS, contact Teva Pharmaceuticals at 1-888-483-8279 or FDA at 1-800-FDA-1088 or www.fda.gov/medwatch.

FULL PRESCRIBING INFORMATION

1 INDICATIONS AND USAGE

1.1 Plaque Psoriasis (PsO)

Ustekinumab-aekn is indicated for the treatment of adults and pediatric patients 6 years of age and older with moderate to severe plaque psoriasis who are candidates for phototherapy or systemic therapy.

1.2 Psoriatic Arthritis (PsA)

Ustekinumab-aekn is indicated for the treatment of adults and pediatric patients 6 years of age and older with active psoriatic arthritis.

1.3 Crohn’s Disease (CD)

Ustekinumab-aekn is indicated for the treatment of adult patients with moderately to severely active Crohn’s disease.

1.4 Ulcerative Colitis

Ustekinumab-aekn is indicated for the treatment of adult patients with moderately to severely active ulcerative colitis.

2 DOSAGE AND ADMINISTRATION

2.1 Recommended Dosage in Plaque Psoriasis

Subcutaneous Adult Dosage Regimen

- For patients weighing 100 kg or less, the recommended dosage is 45 mg initially and 4 weeks later, followed by 45 mg every 12 weeks.
- For patients weighing more than 100 kg, the recommended dosage is 90 mg initially and 4 weeks later, followed by 90 mg every 12 weeks.

In subjects weighing more than 100 kg, 45 mg was also shown to be efficacious. However, 90 mg resulted in greater efficacy in these subjects [see Clinical Studies (14)].

Subcutaneous Pediatric Dosage Regimen

Administer Ustekinumab-aekn subcutaneously at Weeks 0 and 4, then every 12 weeks thereafter.

The recommended dose of Ustekinumab-aekn for pediatric patients 6 years of age and older with plaque psoriasis based on body weight is shown below (Table 1).

Table 1: Recommended Dose of Ustekinumab-aekn for Subcutaneous Injection in Pediatric Patients 6 Years of Age and Older With Plaque Psoriasis
Body Weight of Patient at the Time of Dosing | Recommended Dose
less than 60 kg | 0.75 mg/kg
60 kg to 100 kg | 45 mg
more than 100 kg | 90 mg

For pediatric patients weighing less than 60 kg, the administration volume for the recommended dose (0.75 mg/kg) is shown in Table 2; withdraw the appropriate volume from the vial.

Table 2: Injection volumes of Ustekinumab-aekn 45 mg/0.5 mL Vials for Pediatric Patients 6 Years of Age and Older With Plaque Psoriasis and Pediatric Patients 6 Years of Age and Older With Psoriatic Arthritis* Weighing Less Than 60 kg
Body Weight (kg) at the time of dosing | Dose (mg) | Volume of injection (mL)
15 | 11.3 | 0.12
16 | 12 | 0.13
17 | 12.8 | 0.14
18 | 13.5 | 0.15
19 | 14.3 | 0.16
20 | 15 | 0.17
21 | 15.8 | 0.17
22 | 16.5 | 0.18
23 | 17.3 | 0.19
24 | 18 | 0.20
25 | 18.8 | 0.21
26 | 19.5 | 0.22
27 | 20.3 | 0.22
28 | 21 | 0.23
29 | 21.8 | 0.24
30 | 22.5 | 0.25
31 | 23.3 | 0.26
32 | 24 | 0.27
33 | 24.8 | 0.27
34 | 25.5 | 0.28
35 | 26.3 | 0.29
36 | 27 | 0.3
37 | 27.8 | 0.31
38 | 28.5 | 0.32
39 | 29.3 | 0.32
40 | 30 | 0.33
41 | 30.8 | 0.34
42 | 31.5 | 0.35
43 | 32.3 | 0.36
44 | 33 | 0.37
45 | 33.8 | 0.37
46 | 34.5 | 0.38
47 | 35.3 | 0.39
48 | 36 | 0.4
49 | 36.8 | 0.41
50 | 37.5 | 0.42
51 | 38.3 | 0.42
52 | 39 | 0.43
53 | 39.8 | 0.44
54 | 40.5 | 0.45
55 | 41.3 | 0.46
56 | 42 | 0.46
57 | 42.8 | 0.47
58 | 43.5 | 0.48
59 | 44.3 | 0.49
* Refer to 2.2 Psoriatic Arthritis; Subcutaneous Pediatric Dosage Regimen.

2.2 Recommended Dosage in Psoriatic Arthritis

Subcutaneous Adult Dosage Regimen

- The recommended dosage is 45 mg initially and 4 weeks later, followed by 45 mg every 12 weeks.
- For patients with co-existent moderate-to-severe plaque psoriasis weighing more than 100 kg, the recommended dosage is 90 mg initially and 4 weeks later, followed by 90 mg every 12 weeks.

Subcutaneous Pediatric Dosage Regimen

Administer Ustekinumab-aekn subcutaneously at Weeks 0 and 4, then every 12 weeks thereafter.

The recommended dose of Ustekinumab-aekn for pediatric patients 6 years of age and older with psoriatic arthritis, based on body weight, is shown below (Table 3).

Table 3: Recommended Dose of Ustekinumab-aekn for Subcutaneous Injection in Pediatric Patients 6 Years of Age and Older With Psoriatic Arthritis
Body Weight of Patient at the Time of Dosing | Recommended Dose
less than 60 kg* | 0.75 mg/kg
60 kg or more | 45 mg
greater than 100 kg with co-existent moderate-to-severe plaque psoriasis | 90 mg
* For pediatric patients weighing less than 60 kg, the administration volume for the recommended dose (0.75 mg/kg) is shown in Table 2; withdraw the appropriate volume from the vial.

2.3 Recommended Dosage in Crohn’s Disease and Ulcerative Colitis

Intravenous Induction Adult Dosage Regimen

A single intravenous infusion dose of Ustekinumab-aekn using the weight-based dosage regimen specified in Table 4

[see Instructions for dilution of Ustekinumab-aekn 130 mg vial for intravenous infusion (2.5)].

Table 4: Initial Intravenous Dosage of Ustekinumab-aekn
Body Weight of Patient at the time of dosing | Dose | Number of 130 mg/26 mL (5 mg/mL) Ustekinumab-aekn vials
55 kg or less | 260 mg | 2
more than 55 kg to 85 kg | 390 mg | 3
more than 85 kg | 520 mg | 4

Subcutaneous Maintenance Adult Dosage Regimen

The recommended maintenance dosage is a subcutaneous 90 mg dose administered 8 weeks after the initial intravenous dose, then every 8 weeks thereafter.

2.4 General Considerations for Administration

- Ustekinumab-aekn is intended for use under the guidance and supervision of a healthcare provider. Ustekinumab-aekn should only be administered to patients who will be closely monitored and have regular follow-up visits with a healthcare provider. The appropriate dose should be determined by a healthcare provider using the patient’s current weight at the time of dosing. In pediatric patients, it is recommended that Ustekinumab-aekn be administered by a healthcare provider. If a healthcare provider determines that it is appropriate, a patient may self-inject or a caregiver may inject Ustekinumab-aekn after proper training in subcutaneous injection technique. Instruct patients to follow the directions provided in the Instructions for Use [see Instructions for Use].
- Not made with natural rubber latex.
- It is recommended that each injection be administered at a different anatomic location (such as upper arms, gluteal regions, thighs, or any quadrant of abdomen) than the previous injection, and not into areas where the skin is tender, bruised, erythematous, or indurated. When using the vial, a 1 mL syringe with a 27-gauge, 1/2 inch needle is recommended.
- Prior to administration, visually inspect Ustekinumab-aekn for particulate matter and discoloration. Ustekinumab-aekn is a clear and colorless to slightly yellow solution and free of visible particles. Do not use Ustekinumab-aekn if it is discolored or cloudy, or if other particulate matter is present. Ustekinumab-aekn does not contain preservatives; therefore, discard any unused product remaining in the vial and/or syringe.

2.5 Preparation and Administration of Ustekinumab-aekn 130 mg/26 mL (5 mg/mL) Vial for Intravenous Infusion (Crohn’s Disease and Ulcerative Colitis)

Ustekinumab-aekn solution for intravenous infusion must be diluted, prepared and infused by a healthcare professional using aseptic technique.

1. Calculate the dose and the number of Ustekinumab-aekn vials needed based on patient weight (Table 4). Each 26 mL vial of Ustekinumab-aekn contains 130 mg of ustekinumab-aekn.
2. Withdraw, and then discard a volume of the 0.9% Sodium Chloride Injection from the 250 mL infusion bag equal to the volume of Ustekinumab-aekn to be added (discard 26 mL sodium chloride for each vial of Ustekinumab-aekn needed, for 2 vials- discard 52 mL, for 3 vials- discard 78 mL, 4 vials- discard 104 mL).
3. Withdraw 26 mL of Ustekinumab-aekn from each vial needed and add it to the 250 mL infusion bag. The final volume in the infusion bag should be 250 mL. Gently mix.
4. Visually inspect the diluted solution before infusion. Do not use if visibly opaque particles, discoloration or foreign particles are observed.
5. Infuse the diluted solution over a period of at least one hour. Once diluted, the infusion should be completely administered within four hours of the dilution in the infusion bag.
6. Use only an infusion set with an in-line, sterile, non-pyrogenic, low protein-binding filter (pore size 0.2 micrometer).
7. Do not infuse Ustekinumab-aekn concomitantly in the same intravenous line with other agents.
8. Ustekinumab-aekn does not contain preservatives. Each vial is for one-time use in only one patient. Discard any remaining solution. Dispose any unused medicinal product in accordance with local requirements.

Storage

If necessary, the diluted infusion solution may be kept at room temperature up to 25°C (77°F) for up to 4 hours. Protect the diluted solution from light. Storage time at room temperature begins once the diluted solution has been prepared. The infusion should be completed within 4 hours after the dilution in the infusion bag (cumulative time after preparation including the storage and the infusion period). Do not freeze. Discard any unused portion of the infusion solution.

3 DOSAGE FORMS AND STRENGTHS

Ustekinumab-aekn injection is a clear and colorless to slightly yellow solution and free of visible particles.

Subcutaneous Injection

- Injection: 45 mg/0.5 mL or 90 mg/mL solution in a single-dose prefilled syringe

- Injection: 45 mg/0.5 mL solution in a single-dose vial

Intravenous Infusion

- Injection: 130 mg/26 mL (5 mg/mL) solution in a single-dose vial

4 CONTRAINDICATIONS

Ustekinumab-aekn is contraindicated in patients with clinically significant hypersensitivity to ustekinumab products or to any of the excipients in Ustekinumab-aekn [see Warnings and Precautions (5.5)].

5 WARNINGS AND PRECAUTIONS

5.1 Infections

Ustekinumab products may increase the risk of infections and reactivation of latent infections. Serious bacterial, mycobacterial, fungal, and viral infections were observed in patients receiving ustekinumab products [see Adverse Reactions (6.1, 6.3)].

Serious infections requiring hospitalization, or otherwise clinically significant infections, reported in clinical trials included the following:

- Plaque Psoriasis: diverticulitis, cellulitis, pneumonia, appendicitis, cholecystitis, sepsis, osteomyelitis, viral infections, gastroenteritis, and urinary tract infections.

- Psoriatic arthritis: cholecystitis.

- Crohn’s disease: anal abscess, gastroenteritis, ophthalmic herpes zoster, pneumonia, and listeria meningitis.

- Ulcerative colitis: gastroenteritis, ophthalmic herpes zoster, pneumonia, and listeriosis.

Avoid initiating treatment with Ustekinumab-aekn in patients with any clinically important active infection until the infection resolves or is adequately treated. Consider the risks and benefits of treatment prior to initiating use of Ustekinumab-aekn in patients with a chronic infection or a history of recurrent infection.

Instruct patients to seek medical advice if signs or symptoms suggestive of an infection occur while on treatment with Ustekinumab-aekn and discontinue Ustekinumab-aekn for serious or clinically significant infections until the infection resolves or is adequately treated.

5.2 Theoretical Risk for Vulnerability to Particular Infections

Individuals genetically deficient in IL-12/IL-23 are particularly vulnerable to disseminated infections from mycobacteria (including nontuberculous, environmental mycobacteria), salmonella (including nontyphi strains), and Bacillus Calmette-Guerin (BCG) vaccinations. Serious infections and fatal outcomes have been reported in such patients.

It is not known whether patients with pharmacologic blockade of IL-12/IL-23 from treatment with ustekinumab products may be susceptible to these types of infections. Consider appropriate diagnostic testing, (e.g., tissue culture, stool culture, as dictated by clinical circumstances).

5.3 Pre-treatment Evaluation for Tuberculosis

Evaluate patients for tuberculosis infection prior to initiating treatment with Ustekinumab-aekn.

Avoid administering Ustekinumab-aekn to patients with active tuberculosis infection. Initiate treatment of latent tuberculosis prior to administering Ustekinumab-aekn. Consider anti-tuberculosis therapy prior to initiation of Ustekinumab-aekn in patients with a past history of latent or active tuberculosis in whom an adequate course of treatment cannot be confirmed. Closely monitor patients receiving Ustekinumab-aekn for signs and symptoms of active tuberculosis during and after treatment.

5.4 Malignancies

Ustekinumab products are immunosuppressants and may increase the risk of malignancy. Malignancies were reported among subjects who received ustekinumab in clinical trials [see Adverse Reactions (6.1)]. In rodent models, inhibition of IL-12/IL-23p40 increased the risk of malignancy [see Nonclinical Toxicology (13)].

The safety of ustekinumab products has not been evaluated in patients who have a history of malignancy or who have a known malignancy.

There have been post-marketing reports of the rapid appearance of multiple cutaneous squamous cell carcinomas in patients receiving ustekinumab products who had pre-existing risk factors for developing non- melanoma skin cancer. Monitor all patients receiving Ustekinumab-aekn for the appearance of non-melanoma skin cancer. Closely follow patients greater than 60 years of age, those with a medical history of prolonged immunosuppressant therapy and those with a history of PUVA treatment [see Adverse Reactions (6.1)].

5.5 Serious Hypersensitivity Reactions

Serious hypersensitivity reactions, including anaphylaxis and angioedema, have been reported with ustekinumab products in clinical trials and postmarketing. Some serious hypersensitivity reactions have occurred during the first intravenous dose of ustekinumab products [see Adverse Reactions (6.1, 6.3)]. If a severe or clinically significant hypersensitivity reaction occurs, discontinue Ustekinumab-aekn immediately and initiate appropriate medical treatment [see Contraindications (4)].

5.6 Posterior Reversible Encephalopathy Syndrome (PRES)

Two cases of posterior reversible encephalopathy syndrome (PRES), also known as Reversible Posterior Leukoencephalopathy Syndrome (RPLS), were reported in clinical trials. Cases have also been reported in postmarketing experience in patients with psoriasis, psoriatic arthritis, and Crohn’s disease. Clinical presentation included headaches, seizures, confusion, visual disturbances, and imaging changes consistent with PRES a few days to several months after ustekinumab product initiation. A few cases reported latency of a year or longer. Patients recovered with supportive care following withdrawal of ustekinumab products.

Monitor all patients treated with Ustekinumab-aekn for signs and symptoms of PRES. If PRES is suspected, promptly administer appropriate treatment and discontinue Ustekinumab-aekn.

5.7 Immunizations

Prior to initiating therapy with Ustekinumab-aekn, patients should receive all age-appropriate immunizations as recommended by current immunization guidelines. Patients being treated with Ustekinumab-aekn should avoid receiving live vaccines. Avoid administering BCG vaccines during treatment with Ustekinumab-aekn or for one year prior to initiating treatment or one year following discontinuation of treatment. Caution is advised when administering live vaccines to household contacts of patients receiving Ustekinumab-aekn because of the potential risk for shedding from the household contact and transmission to patient.

Non-live vaccinations received during a course of Ustekinumab-aekn may not elicit an immune response sufficient to prevent disease.

5.8 Noninfectious Pneumonia

Cases of interstitial pneumonia, eosinophilic pneumonia, and cryptogenic organizing pneumonia have been reported during post-approval use of ustekinumab products. Clinical presentations included cough, dyspnea, and interstitial infiltrates following one to three doses. Serious outcomes have included respiratory failure and prolonged hospitalization. Patients improved with discontinuation of therapy and in certain cases administration of corticosteroids. If diagnosis is confirmed, discontinue Ustekinumab-aekn and institute appropriate treatment [see Postmarketing Experience (6.3)].

6 ADVERSE REACTIONS

The following serious adverse reactions are discussed elsewhere in the label:

- Infections [see Warnings and Precautions (5.1)]

- Malignancies [see Warnings and Precautions (5.4)]

- Serious Hypersensitivity Reactions [see Warnings and Precautions (5.5)]

- Posterior Reversible Encephalopathy Syndrome (PRES) [see Warnings and Precautions (5.6)]

- Noninfectious Pneumonia [see Warnings and Precautions (5.8)]

6.1 Clinical Trials Experience

Because clinical trials are conducted under widely varying conditions, adverse reaction rates observed in the clinical trials of a drug cannot be directly compared to rates in the clinical trials of another drug and may not reflect the rates observed in practice.

Adult Subjects with Plaque Psoriasis

The safety data reflect exposure to ustekinumab in 3117 adult subjects with plaque psoriasis, including 2414 exposed for at least 6 months, 1855 exposed for at least one year, 1653 exposed for at least two years, 1569 exposed for at least three years, 1482 exposed for at least four years and 838 exposed for at least five years.

Table 5 summarizes the adverse reactions that occurred at a rate of at least 1% with higher rates in the ustekinumab groups during the placebo-controlled period of Ps STUDY 1 and Ps STUDY 2 [see Clinical Studies (14)].

Table 5: Adverse Reactions, Reported by ≥1% of Subjects with Plaque Psoriasis and at Higher Rates in the ustekinumab groups through Week 12 in Ps STUDY 1 and Ps STUDY 2
 |  | Ustekinumab
 | Placebo | 45 mg | 90 mg
Subjects treated | 665 | 664 | 666
Nasopharyngitis | 51 (8%) | 56 (8%) | 49 (7%)
Upper respiratory tract infection | 30 (5%) | 36 (5%) | 28 (4%)
Headache | 23 (3%) | 33 (5%) | 32 (5%)
Fatigue | 14 (2%) | 18 (3%) | 17 (3%)
Back pain | 8 (1%) | 9 (1%) | 14 (2%)
Dizziness | 8 (1%) | 8 (1%) | 14 (2%)
Pharyngolaryngeal pain | 7 (1%) | 9 (1%) | 12 (2%)
Pruritus | 9 (1%) | 10 (2%) | 9 (1%)
Injection site erythema | 3 (<1%) | 6 (1%) | 13 (2%)
Myalgia | 4 (1%) | 7 (1%) | 8 (1%)
Depression | 3 (<1%) | 8 (1%) | 4 (1%)

Adverse reactions that occurred at rates less than 1% in the controlled period of Ps STUDIES 1 and 2 through week 12 included: cellulitis, herpes zoster, diverticulitis, and certain injection site reactions (pain, swelling, pruritus, induration, hemorrhage, bruising, and irritation).

One case of PRES occurred during clinical trials in adult subjects with plaque psoriasis [see Warnings and Precautions (5.6)].

Infections

In the placebo-controlled period of clinical trials of subjects with plaque psoriasis (average follow-up of 12.6 weeks for subjects receiving placebo and 13.4 weeks for ustekinumab-treated subjects), 27% of ustekinumab-treated subjects reported infections (1.39 per patient-years of follow-up) compared with 24% of subjects receiving placebo (1.21 per patient-years of follow-up). Serious infections occurred in 0.3% of ustekinumab-treated subjects (0.01 per patient-years of follow-up) and in 0.4% of subjects receiving placebo (0.02 per patient-years of follow-up) [see Warnings and Precautions (5.1)].

In the controlled and non-controlled portions of clinical trials in subjects with plaque psoriasis (median follow-up of 3.2 years), representing 8998 patient-years of exposure, 72.3% of ustekinumab-treated subjects reported infections (0.87 per patient-years of follow-up). Serious infections were reported in 2.8% of subjects (0.01 per patient-years of follow-up).

Malignancies

In the controlled and non-controlled portions of clinical trials in subjects with plaque psoriasis (median follow-up of 3.2 years, representing 8998 patient-years of exposure), 1.7% of ustekinumab-treated subjects reported malignancies excluding non-melanoma skin cancers (0.60 per hundred patient-years of follow-up). Non-melanoma skin cancer was reported in 1.5% of ustekinumab-treated subjects (0.52 per hundred patient-years of follow-up) [see Warnings and Precautions (5.4)]. The most frequently observed malignancies other than non-melanoma skin cancer during the clinical trials were: prostate, melanoma, colorectal and breast. Malignancies other than non-melanoma skin cancer in ustekinumab-treated subjects during the controlled and uncontrolled portions of trials were similar in type and number to what would be expected in the general U.S. population according to the SEER database (adjusted for age, gender and race).^1

Pediatric Subjects with Plaque Psoriasis

The safety of ustekinumab was assessed in two trials of pediatric subjects with moderate to severe plaque psoriasis. Ps STUDY 3 evaluated safety for up to 60 weeks in 110 pediatric subjects 12 to 17 years old. Ps STUDY 4 evaluated safety for up to 56 weeks in 44 pediatric subjects 6 to 11 years old. The safety profile in pediatric subjects was similar to the safety profile from trials in adults with plaque psoriasis.

Psoriatic Arthritis

The safety of ustekinumab was assessed in 927 subjects in two randomized, double-blind, placebo-controlled trials in adults with active psoriatic arthritis (PsA). The overall safety profile of ustekinumab in subjects with PsA was consistent with the safety profile seen in clinical trials in adult subjects with plaque psoriasis. A higher incidence of arthralgia, nausea, and dental infections was observed in ustekinumab-treated subjects when compared with placebo-treated subjects (3% vs. 1% for arthralgia and 3% vs. 1% for nausea; 1% vs. 0.6% for dental infections) in the placebo-controlled portions of the PsA clinical trials.

Crohn’s Disease

The safety of ustekinumab was assessed in 1407 subjects with moderately to severely active Crohn’s disease (Crohn’s Disease Activity Index [CDAI] greater than or equal to 220 and less than or equal to 450) in three randomized, double-blind, placebo-controlled, parallel-group, multicenter trials. These 1407 subjects included 40 subjects who received a prior investigational intravenous ustekinumab formulation but were not included in the efficacy analyses. In trials CD-1 and CD-2 there were 470 subjects who received ustekinumab 6 mg/kg as a weight-based single intravenous induction dose and 466 who received placebo [see Dosage and Administration (2.3)]. Subjects who were responders in either trial CD-1 or CD-2 were randomized to receive a subcutaneous maintenance regimen of either 90 mg ustekinumab every 8 weeks, or placebo for 44 weeks in trial CD-3. Subjects in these 3 trials may have received other concomitant therapies including aminosalicylates, immunomodulatory agents [azathioprine (AZA), 6-mercaptopurine (6-MP), methotrexate (MTX)], oral corticosteroids (prednisone or budesonide), and/or antibiotics for their Crohn’s disease [see Clinical Studies (14.4)].

The overall safety profile of ustekinumab was consistent with the safety profile seen in the clinical trials in adult subjects with plaque psoriasis and psoriatic arthritis. Common adverse reactions in trials CD-1 and CD-2 and in trial CD-3 are listed in Tables 6 and 7, respectively.

Table 6: Common Adverse Reactions Through Week 8 in Trials CD-1 and CD-2 occurring in ≥3% of Ustekinumab–Treated Subjects and Higher Than Subjects Receiving Placebo
 | Placebo | Ustekinumab; 6 mg/kg single intravenous; induction dose
 | N=466 | N=470
Vomiting | 3% | 4%

Other less common adverse reactions reported in subjects in trials CD-1 and CD-2 included asthenia (1% vs 0.4%), acne (1% vs 0.4%), and pruritus (2% vs 0.4%).

Table 7: Common Adverse Reactions Through Week 44 in Trial CD-3 occurring in ≥3% of Ustekinumab-Treated Subjects and Higher Than Subjects Receiving Placebo
 | Placebo | Ustekinumab 90 mg subcutaneous maintenance dose every 8 weeks
 | N=133 | N=131
Nasopharyngitis | 8% | 11%
Injection site erythema | 0 | 5%
Vulvovaginal candidiasis/mycotic infection | 1% | 5%
Bronchitis | 3% | 5%
Pruritus | 2% | 4%
Urinary tract infection | 2% | 4%
Sinusitis | 2% | 3%

Infections

In subjects with Crohn’s disease, serious or other clinically significant infections included anal abscess, gastroenteritis, and pneumonia. In addition, listeria meningitis and ophthalmic herpes zoster were reported in one subject each [see Warnings and Precautions (5.1)].

Malignancies

With up to one year of treatment in the Crohn’s disease clinical trials, 0.2% of ustekinumab- treated subjects (0.36 events per hundred patient-years) and 0.2% of placebo-treated subjects (0.58 events per hundred patient- years) developed non-melanoma skin cancer. Malignancies other than non-melanoma skin cancers occurred in 0.2% of ustekinumab-treated subjects (0.27 events per hundred patient-years) and in none of the placebo-treated subjects.

Hypersensitivity Reactions Including Anaphylaxis

In CD trials, two subjects reported hypersensitivity reactions following ustekinumab administration. One subject experienced signs and symptoms consistent with anaphylaxis (tightness of the throat, shortness of breath, and flushing) after a single subcutaneous administration (0.1% of subjects receiving subcutaneous ustekinumab). In addition, one subject experienced signs and symptoms consistent with or related to a hypersensitivity reaction (chest discomfort, flushing, urticaria, and increased body temperature) after the initial intravenous ustekinumab dose (0.08% of subjects receiving intravenous ustekinumab). These subjects were treated with oral antihistamines or corticosteroids and in both cases symptoms resolved within an hour [see Warnings and Precautions (5.5)].

Ulcerative Colitis

The safety of ustekinumab was evaluated in two randomized, double-blind, placebo-controlled clinical trials (UC-1 [IV induction] and UC-2 [SC maintenance]) in 960 adult subjects with moderately to severely active ulcerative colitis [see Clinical Studies (14.5)]. The overall safety profile of ustekinumab in subjects with ulcerative colitis was consistent with the safety profile seen across all approved indications. Adverse reactions reported in at least 3% of ustekinumab-treated subjects and at a higher rate than placebo were:

- Induction (UC-1): nasopharyngitis (7% vs 4%).
- Maintenance (UC-2): nasopharyngitis (24% vs 20%), headache (10% vs 4%), abdominal pain (7% vs 3%), influenza (6% vs 5%), fever (5% vs 4%), diarrhea (4% vs 1%), sinusitis (4% vs 1%), fatigue (4% vs 2%), and nausea (3% vs 2%).

Infections

In subjects with ulcerative colitis, serious or other clinically significant infections included gastroenteritis and pneumonia. In addition, listeriosis and ophthalmic herpes zoster were reported in one subject each [see Warnings and Precautions (5.1)].

Malignancies

With up to one year of treatment in the ulcerative colitis clinical trials, 0.4% of ustekinumab-treated subjects (0.48 events per hundred patient-years) and 0.0% of subjects receiving placebo (0.00 events per hundred patient-years) developed non-melanoma skin cancer. Malignancies other than non-melanoma skin cancers occurred in 0.5% of ustekinumab-treated subjects (0.64 events per hundred patient-years) and 0.2% of subjects receiving placebo (0.40 events per hundred patient-years).

6.2 Immunogenicity

The observed incidence of anti-drug antibodies is highly dependent on the sensitivity and specificity of the assay. Differences in assay methods preclude meaningful comparisons of the incidence of anti-drug antibodies in the studies described below with the incidence of anti-drug antibodies in other studies, including those ustekinumab or of other ustekinumab products.

Approximately 6 to 12.4% of subjects treated with ustekinumab in clinical trials in subjects with plaque psoriasis and psoriatic arthritis developed antibodies to ustekinumab, which were generally low-titer. In clinical trials in subjects with plaque psoriasis, antibodies to ustekinumab were associated with reduced or undetectable serum ustekinumab concentrations and reduced efficacy. In trials in subjects with plaque psoriasis, the majority of subjects who were positive for antibodies to ustekinumab had neutralizing antibodies.

In clinical trials in subjects with Crohn’s disease and ulcerative colitis, 2.9% and 4.6% of subjects, respectively, developed antibodies to ustekinumab when treated with ustekinumab for approximately one year. No apparent association between the development of antibodies to ustekinumab and the development of injection site reactions was seen.

6.3 Postmarketing Experience

The following adverse reactions have been reported during post-approval use of ustekinumab products. Because these reactions are reported voluntarily from a population of uncertain size, it is not always possible to reliably estimate their frequency or establish a causal relationship to ustekinumab product exposure.

Immune system disorders: Hypersensitivity reactions (e.g., anaphylaxis, angioedema, dyspnea, rash, urticaria), including a fatal case that presented with chest tightness and dyspnea during infusion of the first dose.

Infections and infestations: Lower respiratory tract infection (including opportunistic fungal infections and tuberculosis).

Neurological disorders: Posterior Reversible Encephalopathy Syndrome (PRES).

Respiratory, thoracic, and mediastinal disorders: Interstitial pneumonia, eosinophilic pneumonia, and cryptogenic organizing pneumonia.

Skin reactions: Pustular psoriasis, erythrodermic psoriasis, hypersensitivity vasculitis.

7 DRUG INTERACTIONS

7.1 Concomitant Therapies

In trials in subjects with plaque psoriasis the safety of ustekinumab products in combination with immunosuppressive agents or phototherapy has not been evaluated. In trials in subjects with psoriatic arthritis, concomitant MTX use did not appear to influence the safety or efficacy of ustekinumab. In trials in subjects with Crohn’s disease (CD-1 and CD-2) and ulcerative colitis (UC-1), immunomodulators (6-MP, AZA, MTX) were used concomitantly in approximately 30% of subjects and corticosteroids were used concomitantly in approximately 40% and 50% of Crohn’s disease and ulcerative colitis subjects, respectively. Use of these concomitant therapies did not appear to influence the overall safety or efficacy of ustekinumab.

7.2 CYP450 Substrates

The formation of CYP450 enzymes can be suppressed by increased levels of certain cytokines (e.g., IL-1, IL-6, TNFα, IFN) during chronic inflammation. Thus, use of ustekinumab products, antagonists of IL-12 and IL-23, could normalize the formation of CYP450 enzymes. Upon initiation or discontinuation of Ustekinumab-aekn in patients who are receiving concomitant CYP450 substrates, particularly those with a narrow therapeutic index, consider monitoring for therapeutic effect or drug concentration and adjust the individual dosage of the CYP substrate as needed. See the prescribing information of specific CYP substrates.

A CYP-mediated drug interaction effect was not observed in subjects with Crohn’s disease [see Clinical Pharmacology (12.3)].

7.3 Allergen Immunotherapy

Ustekinumab products have not been evaluated in patients who have undergone allergy immunotherapy. Ustekinumab products may decrease the protective effect of allergen immunotherapy (decrease tolerance) which may increase the risk of an allergic reaction to a dose of allergen immunotherapy. Therefore, caution should be exercised in patients receiving or who have received allergen immunotherapy, particularly for anaphylaxis.

8 USE IN SPECIFIC POPULATIONS

8.1 Pregnancy

Risk Summary

Available data from the Organization of Teratology Information Specialists (OTIS)/Mother To Baby Pregnancy Registry, published literature and pharmacovigilance in pregnant women have not identified an ustekinumab-associated risk of major birth defects, miscarriage or other adverse maternal or fetal outcomes (see Data). There are risks to the mother and the fetus associated with inflammatory bowel disease (IBD) in pregnancy. In animal reproductive and developmental toxicity studies, no adverse developmental effects were observed in offspring after administration of ustekinumab to pregnant monkeys at exposures greater than 100 times the maximum recommended human dose (MRHD).

All pregnancies have a background risk of birth defect, loss, or other adverse outcomes. In the U.S. general population, the estimated background risk of major birth defects and miscarriage of clinically recognized pregnancies is 2% to 4% and 15% to 20%, respectively.

Clinical Considerations

Disease-associated Maternal and Embryo/Fetal Risk

Published data suggest that the risk of adverse pregnancy outcomes in women with IBD is associated with increased disease activity. Adverse pregnancy outcomes include preterm delivery (before 37 weeks of gestation), low birth weight (less than 2500 g) infants, and small for gestational age at birth.

Fetal/Neonatal Adverse Reactions

Transport of endogenous IgG antibodies across the placenta increases as pregnancy progresses, and peaks during the third trimester. Therefore, ustekinumab products may be present in infants exposed in utero. The potential clinical impact of ustekinumab products exposure in infants exposed in utero should be considered.

Data

Human Data

An observational pregnancy registry conducted by (OTIS)/Mother To Baby in the U.S. and Canada (enrollment between 2013 and 2019) assessed the risk of major birth defects, pattern of major and minor anomalies in live-born infants, miscarriage, and adverse infant outcomes in women with ustekinumab exposure. In the registry study, there were 101 participants and 107 pregnancies with exposure to ustekinumab (88 prospective; 19 retrospective). Most participants had a primary indication of CD (65.4%) or psoriasis (30.8%). The pregnancy registry did not identify a ustekinumab-associated risk of major birth defects, pattern of major or minor anomalies, increased risk of miscarriage or adverse infant outcomes. Methodological limitations of the registry include small sample size, lack of an internal comparison group, a mix of prospective and retrospective reports, and unmeasured confounders. The conclusions from the pregnancy registry were consistent with the published literature and pharmacovigilance.

Animal Data

Ustekinumab was tested in two embryo-fetal development toxicity studies in cynomolgus monkeys. No teratogenic or other adverse developmental effects were observed in fetuses from pregnant monkeys that were administered ustekinumab subcutaneously twice weekly or intravenously weekly during the period of organogenesis. Serum concentrations of ustekinumab in pregnant monkeys were greater than 100 times the serum concentration in patients treated subcutaneously with 90 mg of ustekinumab weekly for 4 weeks.

In a combined embryo-fetal development and pre- and post-natal development toxicity study, pregnant cynomolgus monkeys were administered subcutaneous doses of ustekinumab twice weekly at exposures greater than 100 times the MRHD from the beginning of organogenesis to Day 33 after delivery. Neonatal deaths occurred in the offspring of one monkey administered ustekinumab at 22.5 mg/kg and one monkey dosed at 45 mg/kg. No ustekinumab-related-effects on functional, morphological, or immunological development were observed in the neonates from birth through six months of age.

8.2 Lactation

Risk Summary

Limited data from published literature suggests that ustekinumab is present in human breast milk. There are no available data on the effects of ustekinumab products on milk production. The effects of local gastrointestinal exposure and limited systemic exposure in the breastfed infant to ustekinumab products are unknown. No adverse effects on the breastfed infant causally related to ustekinumab products have been identified in the published literature or postmarketing experience.

The developmental and health benefits of breastfeeding should be considered along with the mother’s clinical need for Ustekinumab-aekn and any potential adverse effects on the breastfed child from Ustekinumab-aekn or from the underlying maternal condition.

8.4 Pediatric Use

Plaque Psoriasis

The safety and effectiveness of Ustekinumab-aekn have been established for the treatment of moderate to severe plaque psoriasis in pediatric patients 6 years of age and older who are candidates for phototherapy or systemic therapy.

Use of Ustekinumab-aekn in pediatric patients 12 to less than 17 years of age is supported by evidence from a multicenter, randomized, 60 week trial (Ps STUDY 3) of ustekinumab that included a 12 week, double-blind, placebo-controlled, parallel group portion, in 110 pediatric subjects 12 years of age and older [see Adverse Reactions (6.1), Clinical Studies (14.2)].

Use of Ustekinumab-aekn in pediatric patients 6 to 11 years of age is supported by evidence from an open-label, single-arm, efficacy, safety, and pharmacokinetics trial (Ps STUDY 4) of ustekinumab in 44 subjects [see Adverse Reactions (6.1), Pharmacokinetics (12.3)].

The safety and effectiveness of Ustekinumab-aekn have not been established in pediatric patients less than 6 years of age with plaque psoriasis.

Psoriatic Arthritis

The safety and effectiveness of Ustekinumab-aekn have been established for treatment of psoriatic arthritis in pediatric patients 6 years of age and older.

Use of Ustekinumab-aekn in these age groups is supported by evidence from adequate and well controlled trials of ustekinumab in adult subjects with psoriasis and PsA, pharmacokinetic data from adult subjects with psoriasis, adult subjects with PsA and pediatric subjects with psoriasis, and safety data of ustekinumab from two clinical trials in 44 pediatric subjects 6 to 11 years old with psoriasis and 110 pediatric subjects 12 years of age and older with psoriasis. The observed pre-dose (trough) concentrations are generally comparable between adult subjects with psoriasis, adult subjects with PsA and pediatric subjects with psoriasis, and the PK exposure is expected to be comparable between adult and pediatric subjects with PsA [see Adverse Reactions (6.1), Clinical Pharmacology (12.3), and Clinical Studies (14.1, 14.2, 14.3)].

The safety and effectiveness of Ustekinumab-aekn have not been established in pediatric patients less than 6 years old with psoriatic arthritis.

Crohn’s Disease and Ulcerative Colitis

The safety and effectiveness of Ustekinumab-aekn have not been established in pediatric patients with Crohn’s disease or ulcerative colitis.

8.5 Geriatric Use

Of the 6709 subjects exposed to ustekinumab, a total of 340 were 65 years of age or older (183 subjects with plaque psoriasis, 65 subjects with psoriatic arthritis, 58 subjects with Crohn’s disease, and 34 subjects with ulcerative colitis), and 40 subjects were 75 years of age or older. Clinical trials of ustekinumab did not include sufficient numbers of subjects 65 years of age and older to determine whether they respond differently from younger adult subjects.

10 OVERDOSAGE

Single doses up to 6 mg/kg intravenously have been administered in clinical trials without dose-limiting toxicity. In case of overdosage, monitor the patient for any signs or symptoms of adverse reactions or effects and institute appropriate symptomatic treatment immediately. Consider contacting the Poison Help line (1-800- 222-1222) or a medical toxicologist for additional overdose management recommendations.

11 DESCRIPTION

Ustekinumab-aekn, a human IgG1κ monoclonal antibody, is a human interleukin-12 and -23 antagonist. Using DNA recombinant technology, ustekinumab-aekn is produced in a murine cell line (Sp2/0). The manufacturing process contains steps for the clearance of viruses. Ustekinumab-aekn is comprised of 1326 amino acids and has an estimated molecular mass that ranges from 148,079 to 149,690 Daltons.

Ustekinumab-aekn injection is a sterile, preservative-free, clear and colorless to slightly yellow solution free of visible particles with pH of 5.7 to 6.3.

Ustekinumab-aekn for Subcutaneous Use

Available as 45 mg of ustekinumab-aekn in 0.5 mL and 90 mg of ustekinumab-aekn in 1 mL, supplied as a sterile solution in a single-dose prefilled syringe with a 29-gauge fixed 1/2 inch needle and as 45 mg of ustekinumab-aekn in 0.5 mL in a single-dose borosilicate Type I glass vial with a rubber stopper. Not made with natural rubber latex.

Each 0.5 mL prefilled syringe or vial delivers 45 mg ustekinumab-aekn, histidine (0.122 mg), L-histidine monohydrochloride monohydrate (0.507 mg), polysorbate 80 (0.02 mg), sucrose (38 mg) and water for injection (q.s).

Each 1 mL prefilled syringe delivers 90 mg ustekinumab-aekn, histidine (0.243 mg), L-histidine monohydrochloride monohydrate (1.013 mg), polysorbate 80 (0.04 mg), sucrose (76 mg) and water for injection (q.s).

Ustekinumab-aekn for Intravenous Infusion

Available as 130 mg of ustekinumab-aekn in 26 mL, supplied as a single-dose borosilicate type I glass vial with a rubber stopper. Not made with natural rubber latex.

Each 26 mL vial delivers 130 mg ustekinumab-aekn, edetate disodium (0.47 mg), histidine (20.02 mg), L- histidine monohydrochloride monohydrate (27.04 mg), methionine (10.4 mg), polysorbate 80 (10.4 mg), sucrose (2,210 mg), and water for injection (q.s).

12 CLINICAL PHARMACOLOGY

12.1 Mechanism of Action

Ustekinumab products are human IgG1κ monoclonal antibodies that bind with specificity to the p40 protein subunit used by both the IL-12 and IL-23 cytokines. IL-12 and IL-23 are naturally occurring cytokines that are involved in inflammatory and immune responses, such as natural killer cell activation and CD4+ T-cell differentiation and activation. In in vitro models, ustekinumab products were shown to disrupt IL-12 and IL-23 mediated signaling and cytokine cascades by disrupting the interaction of these cytokines with a shared cell- surface receptor chain, IL-12Rβ1. The cytokines IL-12 and IL-23 have been implicated as important contributors to the chronic inflammation that is a hallmark of Crohn’s disease and ulcerative colitis. In animal models of colitis, genetic absence or antibody blockade of the p40 subunit of IL-12 and IL-23, the target of ustekinumab products, was shown to be protective.

12.2 Pharmacodynamics

Plaque Psoriasis

In a small exploratory trial, a decrease was observed in the expression of mRNA of its molecular targets IL-12 and IL-23 in lesional skin biopsies measured at baseline and up to two weeks post-treatment in subjects with plaque psoriasis.

Ulcerative Colitis

In both trial UC-1 (induction) and trial UC-2 (maintenance), a positive relationship was observed between exposure and rates of clinical remission, clinical response, and endoscopic improvement. The response rate approached a plateau at the ustekinumab exposures associated with the recommended dosing regimen for maintenance treatment [see Clinical Studies (14.5)].

12.3 Pharmacokinetics

Absorption

In adult subjects with plaque psoriasis, the median time to reach the maximum serum concentration (Tmax) was 13.5 days and 7 days, respectively, after a single subcutaneous administration of 45 mg (N=22) and 90 mg (N=24) of ustekinumab. In healthy subjects (N=30), the median Tmax value (8.5 days) following a single subcutaneous administration of 90 mg of ustekinumab was comparable to that observed in subjects with plaque psoriasis.

Following multiple subcutaneous doses of ustekinumab in adult subjects with plaque psoriasis, steady-state serum concentrations of ustekinumab were achieved by Week 28. The mean (±SD) steady-state trough serum ustekinumab concentrations were 0.69 ± 0.69 mcg/mL for subjects less than or equal to 100 kg receiving a 45 mg dose and 0.74 ± 0.78 mcg/mL for subjects greater than 100 kg receiving a 90 mg dose. There was no apparent accumulation in serum ustekinumab concentration over time when given subcutaneously every 12 weeks.

Following the recommended intravenous induction dose, mean ±SD peak serum ustekinumab concentration was 125.2 ± 33.6 mcg/mL in subjects with Crohn’s disease, and 129.1 ± 27.6 mcg/mL in subjects with ulcerative colitis. Starting at Week 8, the recommended subcutaneous maintenance dosing of 90 mg ustekinumab was administered every 8 weeks. Steady state ustekinumab concentration was achieved by the start of the second maintenance dose. There was no apparent accumulation in ustekinumab concentration over time when given subcutaneously every 8 weeks. Mean ±SD steady-state trough concentration was 2.5 ± 2.1 mcg/mL in subjects with Crohn’s disease, and 3.3 ± 2.3 mcg/mL in subjects with ulcerative colitis for 90 mg ustekinumab administered every 8 weeks.

Distribution

Population pharmacokinetic analyses showed that the volume of distribution of ustekinumab in the central compartment was 2.7 L (95% CI: 2.69, 2.78) in subjects with Crohn’s disease and 3.0 L (95% CI: 2.96, 3.07) in subjects with ulcerative colitis. The total volume of distribution at steady-state was 4.6 L in subjects with Crohn’s disease and 4.4 L in subjects with ulcerative colitis.

Elimination

The mean (±SD) half-life ranged from 14.9 ± 4.6 to 45.6 ± 80.2 days across all trials in subjects with plaque psoriasis following subcutaneous administration. Population pharmacokinetic analyses showed that the clearance of ustekinumab was 0.19 L/day (95% CI: 0.185, 0.197) in subjects with Crohn’s disease and 0.19 L/day (95% CI: 0.179, 0.192) in subjects with ulcerative colitis with an estimated median terminal half-life of approximately 19 days for both IBD (Crohn’s disease and ulcerative colitis) populations. These results indicate the pharmacokinetics of ustekinumab were similar between subjects with Crohn’s disease and ulcerative colitis.

Metabolism

The metabolic pathway of ustekinumab products has not been characterized. As a human IgG1κ monoclonal antibody, ustekinumab products are expected to be degraded into small peptides and amino acids via catabolic pathways in the same manner as endogenous IgG.

Specific Populations

Weight

When given the same dose, subjects with plaque psoriasis or psoriatic arthritis weighing more than 100 kg had lower median serum ustekinumab concentrations compared with those subjects weighing 100 kg or less. The median trough serum concentrations of ustekinumab in subjects of higher weight (greater than 100 kg) in the 90 mg group were comparable to those in subjects of lower weight (100 kg or less) in the 45 mg group.

Age: Geriatric Population

A population pharmacokinetic analysis (N=106/1937 subjects with plaque psoriasis greater than or equal to 65 years old) was performed to evaluate the effect of age on the pharmacokinetics of ustekinumab. There were no apparent changes in pharmacokinetic parameters (clearance and volume of distribution) in subjects older than 65 years old.

Age: Pediatric Population

Following multiple recommended doses of ustekinumab in pediatric subjects 6 years of age and older with plaque psoriasis, steady-state serum concentrations of ustekinumab were achieved by Week 28. At Week 28, the mean ±SD steady-state trough serum ustekinumab concentrations were 0.36 ± 0.26 mcg/mL and 0.54 ± 0.43 mcg/mL, respectively, in pediatric subjects 6 to 11 years of age and pediatric subjects 12 years of age and older.

Overall, the observed steady-state ustekinumab trough concentrations in pediatric subjects with plaque psoriasis were within the range of those observed for adult subjects with plaque psoriasis and adult subjects with PsA after administration of ustekinumab.

Drug Interaction Studies

The effects of IL-12 or IL-23 on the regulation of CYP450 enzymes were evaluated in an in vitro study using human hepatocytes, which showed that IL-12 and/or IL-23 at levels of 10 ng/mL did not alter human CYP450 enzyme activities (CYP1A2, 2B6, 2C9, 2C19, 2D6, or 3A4).

No clinically significant changes in exposure of caffeine (CYP1A2 substrate), warfarin (CYP2C9 substrate), omeprazole (CYP2C19 substrate), dextromethorphan (CYP2D6 substrate), or midazolam (CYP3A substrate) were observed when used concomitantly with ustekinumab at the approved recommended dosage in subjects with Crohn’s disease [see Drug Interactions (7.2)].

Population pharmacokinetic analyses indicated that the clearance of ustekinumab was not impacted by concomitant MTX, NSAIDs, and oral corticosteroids, or prior exposure to a TNF blocker in subjects with psoriatic arthritis.

In subjects with Crohn’s disease and ulcerative colitis, population pharmacokinetic analyses did not indicate changes in ustekinumab clearance with concomitant use of corticosteroids or immunomodulators (AZA, 6-MP, or MTX); and serum ustekinumab concentrations were not impacted by concomitant use of these medications.

13 NONCLINICAL TOXICOLOGY

13.1 Carcinogenesis, Mutagenesis, Impairment of Fertility

Animal studies have not been conducted to evaluate the carcinogenic or mutagenic potential of ustekinumab products. Published literature showed that administration of murine IL-12 caused an anti-tumor effect in mice that contained transplanted tumors and IL-12/IL-23p40 knockout mice or mice treated with anti-IL-12/IL-23p40 antibody had decreased host defense to tumors. Mice genetically manipulated to be deficient in both IL-12 and IL-23 or IL-12 alone developed UV-induced skin cancers earlier and more frequently compared to wild-type mice. The relevance of these experimental findings in mouse models for malignancy risk in humans is unknown.

No effects on fertility were observed in male cynomolgus monkeys that were administered ustekinumab at subcutaneous doses up to 45 mg/kg twice weekly (45 times the MRHD on a mg/kg basis) prior to and during the mating period. However, fertility and pregnancy outcomes were not evaluated in mated females.

No effects on fertility were observed in female mice that were administered an analogous IL-12/IL-23p40 antibody by subcutaneous administration at doses up to 50 mg/kg, twice weekly, prior to and during early pregnancy.

13.2 Animal Toxicology and/or Pharmacology

In a 26-week toxicology study, one out of 10 monkeys subcutaneously administered 45 mg/kg ustekinumab twice weekly for 26 weeks had a bacterial infection.

14 CLINICAL STUDIES

14.1 Adult Subjects with Plaque Psoriasis

Two multicenter, randomized, double-blind, placebo-controlled trials (Ps STUDY 1 and Ps STUDY 2) enrolled a total of 1996 subjects 18 years of age and older with plaque psoriasis who had a minimum body surface area involvement of 10%, and Psoriasis Area and Severity Index (PASI) score ≥12, and who were candidates for phototherapy or systemic therapy. Subjects with guttate, erythrodermic, or pustular psoriasis were excluded from the trials.

Ps STUDY 1 enrolled 766 subjects and Ps STUDY 2 enrolled 1230 subjects. The trials had the same design through Week 28. In both trials, subjects were randomized in equal proportion to placebo, 45 mg or 90 mg of ustekinumab. Subjects randomized to ustekinumab received 45 mg or 90 mg doses, regardless of weight, at Weeks 0, 4, and 16. Subjects randomized to receive placebo at Weeks 0 and 4 crossed over to receive ustekinumab (either 45 mg or 90 mg) at Weeks 12 and 16.

In both trials, subjects in all treatment groups had a median baseline PASI score ranging from approximately 17 to 18. Baseline PGA score was marked or severe in 44% of subjects in Ps STUDY 1 and 40% of subjects in Ps STUDY 2. Approximately two-thirds of all subjects had received prior phototherapy, 69% had received either prior conventional systemic or biologic therapy for the treatment of psoriasis, with 56% receiving prior conventional systemic therapy and 43% receiving prior biologic therapy. A total of 28% of subjects had a history of psoriatic arthritis.

In both trials, the endpoints were the proportion of subjects who achieved at least a 75% reduction in PASI score (PASI 75) from baseline to Week 12 and treatment success (cleared or minimal) on the Physician’s Global Assessment (PGA). The PGA is a 6-category scale ranging from 0 (cleared) to 5 (severe) that indicates the physician’s overall assessment of psoriasis focusing on plaque thickness/induration, erythema, and scaling.

Clinical Response

The results of Ps STUDY 1 and Ps STUDY 2 are presented in Table 8 below.

Table 8: Clinical Outcomes at Week 12 in Adult Subjects with Plaque Psoriasis in Ps STUDY 1 and Ps STUDY 2
 |  | Ps STUDY 1 |  |  | Ps STUDY 2
 |  | Ustekinumab |  |  | Ustekinumab
 | Placebo | 45 mg | 90 mg | Placebo | 45 mg | 90 mg
Subjects randomized | 255 | 255 | 256 | 410 | 409 | 411
PASI 75 response | 8 (3%) | 171 (67%) | 170 (66%) | 15 (4%) | 273 (67%) | 311 (76%)
PGA of Cleared or Minimal | 10 (4%) | 151 (59%) | 156 (61%) | 18 (4%) | 277 (68%) | 300 (73%)

Examination of age, gender, and race subgroups did not identify differences in response to ustekinumab among these subgroups.

In subjects who weighed 100 kg or less, response rates were comparable with both the 45 mg and 90 mg doses; however, in subjects who weighed greater than 100 kg, higher response rates were seen with 90 mg dosing compared with 45 mg dosing (Table 9 below).

Table 9: Clinical Outcomes by Weight at Week 12 in Adult Subjects with Plaque Psoriasis in Ps STUDY 1 and Ps STUDY 2
 | Ps STUDY 1 |  |  | Ps STUDY 2
 |  | Ustekinumab |  |  | Ustekinumab
 | Placebo | 45 mg | 90 mg | Placebo | 45 mg | 90 mg
Subjects randomized | 255 | 255 | 256 | 410 | 409 | 411
PASI 75 response*
≤100 kg | 4% | 74% | 65% | 4% | 73% | 78%
 | 6/166 | 124/168 | 107/164 | 12/290 | 218/297 | 225/289
>100 kg | 2% | 54% | 68% | 3% | 49% | 71%
 | 2/89 | 47/87 | 63/92 | 3/120 | 55/112 | 86/121
PGA of Cleared or Minimal*
≤100 kg | 4% | 64% | 63% | 5% | 74% | 75%
 | 7/166 | 108/168 | 103/164 | 14/290 | 220/297 | 216/289
>100 kg | 3% | 49% | 58% | 3% | 51% | 69%
 | 3/89 | 43/87 | 53/92 | 4/120 | 57/112 | 84/121
* Subjects were dosed with trial medication at Weeks 0 and 4.

Subjects in Ps STUDY 1 who were PASI 75 responders at both Weeks 28 and 40 were re-randomized at Week 40 to either continued dosing of ustekinumab (ustekinumab at Week 40) or to withdrawal of therapy (placebo at Week 40). At Week 52, 89% (144/162) of subjects re-randomized to ustekinumab treatment were PASI 75 responders compared with 63% (100/159) of subjects re-randomized to placebo (treatment withdrawal after Week 28 dose). The median time to loss of PASI 75 response among the subjects randomized to treatment withdrawal was 16 weeks.

14.2 Pediatric Subjects with Plaque Psoriasis

A multicenter, randomized, double blind, placebo-controlled trial (Ps STUDY 3) enrolled 110 pediatric subjects 12 years of age and older with a minimum BSA involvement of 10%, a PASI score greater than or equal to 12, and a PGA score greater than or equal to 3, who were candidates for phototherapy or systemic therapy and whose disease was inadequately controlled by topical therapy.

Subjects were randomized to receive placebo (n = 37), the recommended dose of ustekinumab (n = 36), or one-half the recommended dose of ustekinumab (n = 37) by subcutaneous injection at Weeks 0 and 4 followed by dosing every 12 weeks (q12w). The recommended dose of ustekinumab was 0.75 mg/kg for subjects weighing
less than 60 kg, 45 mg for subjects weighing 60 kg to 100 kg, and 90 mg for subjects weighing greater than 100 kg. At Week 12, subjects who received placebo were crossed over to receive ustekinumab at the recommended dose or one-half the recommended dose.

Of the pediatric subjects, approximately 63% had prior exposure to phototherapy or conventional systemic therapy and approximately 11% had prior exposure to biologics.

The endpoints were the proportion of subjects who achieved a PGA score of cleared (0) or minimal (1), PASI 75, and PASI 90 at Week 12. Subjects were followed for up to 60 weeks following first administration of trial agent.

Clinical Response
The efficacy results at Week 12 for Ps STUDY 3 are presented in Table 10.

Table 10: Efficacy Results at Week 12 in Pediatric Subjects 12 Years of Age and Older with Plaque Psoriasis in Ps STUDY 3
 | Ps STUDY 3
 | Placebo | Ustekinumab*
 | n (%) | n (%)
N | 37 | 36
PGA
PGA of cleared (0) or minimal (1) | 2 (5.4%) | 25 (69.4%)
PASI
PASI 75 responders | 4 (10.8%) | 29 (80.6%)
PASI 90 responders | 2 (5.4%) | 22 (61.1%)
* Using the weight-based dosage regimen specified in Table 1 and Table 2.

14.3 Psoriatic Arthritis

The safety and efficacy of ustekinumab was assessed in 927 subjects (PsA STUDY 1, n=615; PsA STUDY 2, n=312), in two randomized, double-blind, placebo-controlled trials in adult subjects 18 years of age and older with active PsA (≥5 swollen joints and ≥5 tender joints) despite nonsteroidal anti-inflammatory (NSAID) or disease modifying antirheumatic (DMARD) therapy. Subjects in these trials had a diagnosis of PsA for at least 6 months. Subjects with each subtype of PsA were enrolled, including polyarticular arthritis with the absence of rheumatoid nodules (39%), spondylitis with peripheral arthritis (28%), asymmetric peripheral arthritis (21%), distal interphalangeal involvement (12%) and arthritis mutilans (0.5%). Over 70% and 40% of the patients, respectively, had enthesitis and dactylitis at baseline.

Subjects were randomized to receive treatment with ustekinumab 45 mg, 90 mg, or placebo subcutaneously at Weeks 0 and 4 followed by every 12 weeks (q12w) dosing. Approximately 50% of subjects continued on stable doses of MTX (≤25 mg/week). The primary endpoint was the percentage of subjects achieving ACR 20 response at Week 24.

In PsA STUDY 1 and PsA STUDY 2, 80% and 86% of the subjects, respectively, had been previously treated with DMARDs. In PsA STUDY 1, previous treatment with anti-tumor necrosis factor (TNF)-α agent was not allowed. In PsA STUDY 2, 58% (n=180) of the subjects had been previously treated with TNF blocker, of whom over 70% had discontinued their TNF blocker treatment for lack of efficacy or intolerance at any time.

Clinical Response

In both trials, a greater proportion of subjects achieved ACR 20, ACR 50 and PASI 75 response in the ustekinumab 45 mg and 90 mg groups compared to placebo at Week 24 (see Table 11). ACR 70 responses were also higher in the ustekinumab 45 mg and 90 mg groups, although the difference was only numerical (p=NS) in STUDY 2. Responses were consistent in subjects treated with ustekinumab alone or in combination with methotrexate. Responses were similar in subjects regardless of prior TNFα exposure.

Table 11: ACR 20, ACR 50, ACR 70 and PASI 75 Responses In PsA STUDY 1 And PsA STUDY 2 At Week 24
 | PsA STUDY 1 |  |  | PsA STUDY 2
 |  | Ustekinumab |  |  | Ustekinumab
 | Placebo | 45 mg | 90 mg | Placebo | 45 mg | 90 mg
Number of subjects randomized | 206 | 205 | 204 | 104 | 103 | 105
ACR 20 response, N (%) | 47 (23%) | 87 (42%) | 101 (50%) | 21 (20%) | 45 (44%) | 46 (44%)
ACR 50 response, N (%) | 18 (9%) | 51 (25%) | 57 (28%) | 7 (7%) | 18 (17%) | 24 (23%)
ACR 70 response, N (%) | 5 (2%) | 25 (12%) | 29 (14%) | 3 (3%) | 7 (7%) | 9 (9%)
Number of subjects with ≥ 3% BSAa | 146 | 145 | 149 | 80 | 80 | 81
PASI 75 response, N (%) | 16 (11%) | 83 (57%) | 93 (62%) | 4 (5%) | 41 (51%) | 45 (56%)
a Number of subjects with ≥ 3% BSA psoriasis skin involvement at baseline

The percent of subjects achieving ACR 20 responses by visit is shown in Figure 1.

Figure 1: Percent of subjects achieving ACR 20 response through Week 24

PsA STUDY 1

The results of the components of the ACR response criteria are shown in Table 12.

Table 12: Mean Change From Baseline In ACR Components At Week 24
 |  | PsA STUDY 1
 | Ustekinumab
 | Placebo; (N = 206) | 45 mg; (N = 205) | 90 mg; (N = 204)
Number of swollen jointsa
Baseline | 15 | 12 | 13
Mean Change at Week 24 | -3 | -5 | -6
Number of tender jointsb
Baseline | 25 | 22 | 23
Mean Change at Week 24 | -4 | -8 | -9
Subject’s assessment of painc
Baseline | 6.1 | 6.2 | 6.6
Mean Change at Week 24 | -0.5 | -2.0 | -2.6
Subject global assessmentc
Baseline | 6.1 | 6.3 | 6.4
Mean Change at Week 24 | -0.5 | -2.0 | -2.5
Physician global assessmentc
Baseline | 5.8 | 5.7 | 6.1
Mean Change at Week 24 | -1.4 | -2.6 | -3.1
Disability index (HAQ)d
Baseline | 1.2 | 1.2 | 1.2
Mean Change at Week 24 | -0.1 | -0.3 | -0.4
CRP (mg/dL)e
Baseline | 1.6 | 1.7 | 1.8
Mean Change at Week 24 | 0.01 | -0.5 | -0.8
a Number of swollen joints counted (0-66)
b Number of tender joints counted (0-68)
c Visual analogue scale; 0= best, 10=worst.
d Disability Index of the Health Assessment Questionnaire; 0 = best, 3 = worst, measures the patient’s ability to perform the following: dress/groom, arise, eat, walk, reach, grip, maintain hygiene, and maintain daily activity.
e CRP: (Normal Range 0.0-1.0 mg/dL)

An improvement in enthesitis and dactylitis scores was observed in each ustekinumab group compared with placebo at Week 24.

Physical Function

Ustekinumab-treated subjects showed improvement in physical function compared to subjects receiving placebo as assessed by HAQ-DI at Week 24. In both trials, the proportion of HAQ-DI responders (≥0.3 improvement in HAQ-DI score) was greater in the ustekinumab 45 mg and 90 mg groups compared to placebo at Week 24.

14.4 Crohn’s Disease

Ustekinumab was evaluated in three randomized, double-blind, placebo-controlled clinical trials in adult subjects with moderately to severely active Crohn’s disease (Crohn’s Disease Activity Index [CDAI] score of 220 to 450). There were two 8-week intravenous induction trials (CD-1 and CD-2) followed by a 44-week subcutaneous randomized withdrawal maintenance trial (CD-3) representing 52 weeks of therapy. Subjects in CD-1 had failed or were intolerant to treatment with one or more TNF blockers, while subjects in CD-2 had failed or were intolerant to treatment with immunomodulators or corticosteroids, but never failed treatment with a TNF blocker.

Trials CD-1 and CD-2

In trials CD-1 and CD-2, 1409 subjects were randomized, of whom 1368 (CD-1, n=741; CD-2, n=627) were included in the final efficacy analysis. Induction of clinical response (defined as a reduction in CDAI score of greater than or equal to 100 points or CDAI score of less than 150) at Week 6 and clinical remission (defined as a CDAI score of less than 150) at Week 8 were evaluated. In both trials, subjects were randomized to receive a single intravenous administration of ustekinumab at either approximately 6 mg/kg, placebo (see Table 4), or 130 mg (a lower dose than recommended).

In trial CD-1, subjects had failed or were intolerant to prior treatment with a TNF blocker: 29% subjects had an inadequate initial response (primary non-responders), 69% responded but subsequently lost response (secondary non-responders) and 36% were intolerant to a TNF blocker. Of these subjects, 48% failed or were intolerant to one TNF blocker and 52% had failed 2 or 3 prior TNF blockers. At baseline and throughout the trial, approximately 46% of the subjects were receiving corticosteroids and 31% of the subjects were receiving immunomodulators (AZA, 6-MP, MTX). The median baseline CDAI score was 319 in the ustekinumab approximately 6 mg/kg group and 313 in the placebo group.

In trial CD-2, subjects had failed or were intolerant to prior treatment with corticosteroids (81% of subjects), at least one immunomodulator (6-MP, AZA, MTX; 68% of subjects), or both (49% of subjects). Additionally, 69% never received a TNF blocker and 31% previously received but had not failed a TNF blocker. At baseline, and throughout the trial, approximately 39% of the subjects were receiving corticosteroids and 35% of the subjects were receiving immunomodulators (AZA, 6-MP, MTX). The median baseline CDAI score was 286 in the ustekinumab and 290 in the placebo group.

In these induction trials, a greater proportion of subjects treated with ustekinumab (at the recommended dose of approximately 6 mg/kg dose) achieved clinical response at Week 6 and clinical remission at Week 8 compared to placebo (see Table 13 for clinical response and remission rates). Clinical response and remission were significant as early as Week 3 in ustekinumab-treated subjects and continued to improve through Week 8.

Table 13: Induction of Clinical Response and Remission in CD-1* and CD-2**
 |  | CD-1; n = 741 |  |  | CD-2; n = 627
 | Placebo; N = 247 | Ustekinumab†; N = 249 | Treatment difference; and 95% CI | Placebo; N = 209 | Ustekinumab†; N = 209 | Treatment difference; and 95% CI
Clinical Response; (100 point), Week 6 | 53 (21%) | 84 (34%)a | 12% | 60 (29%) | 116 (56%)b | 27%
Clinical Response; (100 point), Week 6 |  |  | (4%, 20%) |  |  | (18%, 36%)
Clinical Remission,; Week 8 | 18 (7%) | 52 (21%)b | 14% | 41 (20%) | 84 (40%)b | 21%
Clinical Remission,; Week 8 |  |  | (8%, 20%) |  |  | (12%, 29%)
Clinical Response; (100 point), Week 8 | 50 (20%) | 94 (38%)b | 18% | 67 (32%) | 121 (58%)b | 26%
Clinical Response; (100 point), Week 8 |  |  | (10%, 25%) |  |  | (17%, 35%)
70 Point Response,; Week 6 | 75 (30%) | 109 (44%)a | 13% | 81 (39%) | 135 (65%)b | 26%
70 Point Response,; Week 6 |  |  | (5%, 22%) |  |  | (17%, 35%)
70 Point Response,; Week 3 | 67 (27%) | 101 (41%)a | 13% | 66 (32%) | 106 (51%)b | 19%
70 Point Response,; Week 3 |  |  | (5%, 22%) |  |  | (10%, 28%)
Clinical remission is defined as CDAI score < 150; Clinical response is defined as reduction in CDAI score by at least 100 points or being in clinical remission: 70 point response is defined as reduction in CDAI score by at least 70 points
* Patient population consisted of subjects who failed or were intolerant to TNF blocker therapy
** Patient population consisted of subjects who failed or were intolerant to corticosteroids or immunomodulators (e.g., 6-MP, AZA, MTX) and previously received but not failed a TNF blocker or were never treated with a TNF blocker.
† Infusion dose of ustekinumab using the weight-based dosage regimen specified in Table 4.
a 0.001≤ p < 0.01
b p < 0.001

Trial CD-3

The maintenance trial (CD-3), evaluated 388 subjects who achieved clinical response (≥100 point reduction in CDAI score) at Week 8 with either induction dose of ustekinumab in trials CD-1 or CD-2. Subjects were randomized to receive a subcutaneous maintenance regimen of either 90 mg ustekinumab every 8 weeks or placebo for 44 weeks (see Table 14).

Table 14: Clinical Response and Remission In CD-3 (Week 44; 52 Weeks From Initiation Of The Induction Dose)
 |  | 90 mg Ustekinumab | Treatment
 | Placebo* | every 8 weeks | difference and
 | N = 131† | N = 128† | 95% CI
Clinical Remission | 47 (36%) | 68 (53%)a | 17% (5%, 29%)
Clinical Response | 58 (44%) | 76 (59%)b | 15% (3%, 27%)
Clinical Remission in patients in remission at the start of maintenance therapy** | 36/79 (46%) | 52/78 (67%)a | 21% (6%, 36%)
Clinical remission is defined as CDAI score < 150; Clinical response is defined as reduction in CDAI of at least 100 points or being in clinical remission
* The placebo group consisted of subjects who were in response to ustekinumab and were randomized to receive placebo at the start of maintenance therapy.
** Subjects in remission at the end of maintenance therapy who were in remission at the start of maintenance therapy. This does not account for any other time point during maintenance therapy.
† Subjects who achieved clinical response to ustekinumab at the end of the induction trial.
a p < 0.01
b 0.01≤ p < 0.05

At Week 44, 47% of subjects who received ustekinumab were corticosteroid-free and in clinical remission, compared to 30% of subjects in the placebo group.

At Week 0 of trial CD-3, 34/56 (61%) ustekinumab-treated subjects who previously failed or were intolerant to TNF blocker therapies were in clinical remission and 23/56 (41%) of these subjects were in clinical remission at Week 44. In the placebo arm, 27/61 (44%) subjects were in clinical remission at Week 0 while 16/61 (26%) of these subjects were in remission at Week 44.

At Week 0 of trial CD-3, 46/72 (64%) ustekinumab-treated subjects who had previously failed immunomodulator therapy or corticosteroids (but not TNF blockers) were in clinical remission and 45/72 (63%) of these subjects were in clinical remission at Week 44. In the placebo arm, 50/70 (71%) of these subjects were in clinical remission at Week 0 while 31/70 (44%) were in remission at Week 44. In the subset of these subjects who were also naïve to TNF blockers, 34/52 (65%) of ustekinumab-treated subjects were in clinical remission at Week 44 as compared to 25/51 (49%) in the placebo arm.

Subjects who were not in clinical response 8 weeks after ustekinumab induction were not included in the primary efficacy analyses for trial CD-3; however, these subjects were eligible to receive a 90 mg subcutaneous injection of ustekinumab upon entry into trial CD-3. Of these subjects, 102/219 (47%) achieved clinical response eight weeks later and were followed for the duration of the trial.

14.5 Ulcerative Colitis

Ustekinumab was evaluated in two randomized, double-blind, placebo-controlled clinical trials [UC-1 and UC-2 (NCT02407236)] in adult subjects with moderately to severely active ulcerative colitis who had an inadequate response to or failed to tolerate a biologic (i.e., TNF blocker and/or vedolizumab), corticosteroids, and/or 6-MP or AZA therapy. The 8-week intravenous induction trial (UC-1) was followed by the 44-week subcutaneous randomized withdrawal maintenance trial (UC-2) for a total of 52 weeks of therapy.

Disease assessment was based on the Mayo score, which ranged from 0 to 12 and has four subscores that were each scored from 0 (normal) to 3 (most severe): stool frequency, rectal bleeding, findings on centrally-reviewed endoscopy, and physician global assessment. Moderately to severely active ulcerative colitis was defined at baseline (Week 0) as Mayo score of 6 to 12, including a Mayo endoscopy subscore ≥2. An endoscopy score of 2 was defined by marked erythema, absent vascular pattern, friability, erosions; and a score of 3 was defined by spontaneous bleeding, ulceration. At baseline, subjects had a median Mayo score of 9, with 84% of subjects having moderate disease (Mayo score 6-10) and 15% having severe disease (Mayo score 11-12).

Subjects in these trials may have received other concomitant therapies including aminosalicylates, immunomodulatory agents (AZA, 6-MP, or MTX), and oral corticosteroids (prednisone).

Trial UC-1

In UC-1, 961 subjects were randomized at Week 0 to a single intravenous administration of ustekinumab of approximately 6 mg/kg, 130 mg (a lower dose than recommended), or placebo. Subjects enrolled in UC-1 had to have failed therapy with corticosteroids, immunomodulators or at least one biologic. A total of 51% had failed at least one biologic and 17% had failed both a TNF blocker and an integrin receptor blocker. Of the total population, 46% had failed corticosteroids or immunomodulators but were biologic-naïve and an additional 3% had previously received but had not failed a biologic. At induction baseline and throughout the trial, approximately 52% subjects were receiving oral corticosteroids, 28% subjects were receiving immunomodulators (AZA, 6-MP, or MTX) and 69% subjects were receiving aminosalicylates.

The primary endpoint was clinical remission at Week 8. Clinical remission with a definition of: Mayo stool frequency subscore of 0 or 1, Mayo rectal bleeding subscore of 0 (no rectal bleeding), and Mayo endoscopy subscore of 0 or 1 (Mayo endoscopy subscore of 0 defined as normal or inactive disease and Mayo subscore of 1 defined as presence of erythema, decreased vascular pattern and no friability) is provided in Table 15.

The secondary endpoints were clinical response, endoscopic improvement, and histologic- endoscopic mucosal improvement. Clinical response with a definition of (≥ 2 points and ≥ 30% decrease in modified Mayo score, defined as 3-component Mayo score without the Physician’s Global Assessment, with either a decrease from baseline in the rectal bleeding subscore ≥1 or a rectal bleeding subscore of 0 or 1), endoscopic improvement with a definition of Mayo endoscopy subscore of 0 or 1, and histologic-endoscopic mucosal improvement with a definition of combined endoscopic improvement and histologic improvement of the colon tissue [neutrophil infiltration in <5% of crypts, no crypt destruction, and no erosions, ulcerations, or granulation tissue]) are provided in Table 15.

In UC-1, a significantly greater proportion of subjects treated with ustekinumab (at the recommended dose of approximately 6 mg/kg dose) were in clinical remission and response and achieved endoscopic improvement and histologic-endoscopic mucosal improvement compared to placebo (see Table 15).

Table 15: Proportion of Subjects Meeting Efficacy Endpoints at Week 8 in UC-1
Endpoint | Placebo; N = 319 |  | Ustekinumab†; N = 322 |  | Treatment difference and; 97.5% CI a
 | N | % | N | % | Treatment difference and; 97.5% CI a
Clinical Remission* | 22 | 7% | 62 | 19% | 12%; (7%, 18%) b
Bio-naïve⸸ | 14/151 | 9% | 36/147 | 24%
Prior biologic failure | 7/161 | 4% | 24/166 | 14%
Endoscopic Improvement§ | 40 | 13% | 80 | 25% | 12%
Bio-naïve⸸ | 28/151 | 19% | 43/147 | 29% | (6%, 19%)b
Prior biologic failure | 11/161 | 7% | 34/166 | 20%
Clinical Response† | 99 | 31% | 186 | 58% | 27% (18%, 35%) b
Bio-naïve⸸ | 55/151 | 36% | 94/147 | 64%
Prior biologic failure | 42/161 | 26% | 86/166 | 52%
Histologic-Endoscopic Mucosal Improvement‡ | 26 | 8% | 54 | 17% | 9% (3%, 14%) b
Bio-naïve⸸ | 19/151 | 13% | 30/147 | 20%
Prior biologic failure | 6/161 | 4% | 21/166 | 13%
† Infusion dose of ustekinumab using the weight-based dosage regimen specified in Table 4.
⸸ An additional 7 subjects on placebo and 9 subjects on ustekinumab (6 mg/kg) had been exposed to, but had not failed, biologics.
* Clinical remission was defined as Mayo stool frequency subscore of 0 or 1, Mayo rectal bleeding subscore of 0, and Mayo endoscopy subscore of 0 or 1 (modified so that 1 does not include friability).
§ Endoscopic improvement was defined as Mayo endoscopy subscore of 0 or 1 (modified so that 1 does not include friability).
† Clinical response was defined as a decrease from baseline in the modified Mayo score by ≥30% and ≥2 points, with either a decrease from baseline in the rectal bleeding subscore ≥1 or a rectal bleeding subscore of 0 or 1.
‡ Histologic-endoscopic mucosal improvement was defined as combined endoscopic improvement (Mayo endoscopy subscore of 0 or 1) and histologic improvement of the colon tissue (neutrophil infiltration in <5% of crypts, no crypt destruction, and no erosions, ulcerations, or granulation tissue).
a Adjusted treatment difference (97.5% CI)
b p < 0.001

The relationship of histologic-endoscopic mucosal improvement, as defined in UC-1, at Week 8 to disease progression and long-term outcomes was not evaluated during UC-1.

Rectal Bleeding and Stool Frequency Subscores

Decreases in rectal bleeding and stool frequency subscores were observed as early as Week 2 in ustekinumab-treated subjects.

Trial UC-2

The maintenance trial (UC-2) evaluated 523 subjects who achieved clinical response 8 weeks following the intravenous administration of either induction dose of ustekinumab in UC-1. These subjects were randomized to receive a subcutaneous maintenance regimen of either 90 mg ustekinumab every 8 weeks, or every 12 weeks (a lower dose than recommended), or placebo for 44 weeks. The primary endpoint was the proportion of subjects in clinical remission at Week 44. The secondary endpoints included the proportion of subjects maintaining clinical response at Week 44, the proportion of subjects with endoscopic improvement at Week 44, the proportion of subjects with corticosteroid-free clinical remission at Week 44, and the proportion of subjects maintaining clinical remission at Week 44 among subjects who achieved clinical remission 8 weeks after induction.

Results of the primary and secondary endpoints at Week 44 in subjects treated with ustekinumab at the recommended dosage (90 mg every 8 weeks) compared to the placebo are shown in Table 16.

Table 16: Efficacy Endpoints of Maintenance at Week 44 in UC-2 (52 Weeks from Initiation of the Induction Dose)
Endpoint | Placebo*; N = 175† |  | 90 mg Ustekinumab; every 8 weeks; N = 176 |  | Treatment difference and; 95% CI
Endpoint | N | % | N | %
Clinical Remission** | 46 | 26% | 79 | 45% | 19%; (9%, 28%) a
Bio-naïve⸸ | 30/84 | 36% | 39/79 | 49%
Prior biologic failure | 16/88 | 18% | 37/91 | 41%
Maintenance of Clinical Response at Week 44† | 84 | 48% | 130 | 74% | 26%; (16%, 36%) a
Bio-naïve⸸ | 49/84 | 58% | 62/79 | 78%
Prior biologic failure | 35/88 | 40% | 64/91 | 70%
Endoscopic Improvement§ | 47 | 27% | 83 | 47% | 20%; (11%, 30%) a
Bio-naïve⸸ | 29/84 | 35% | 42/79 | 53%
Prior biologic failure | 18/88 | 20% | 38/91 | 42%
Corticosteroid-free Clinical Remission‡ | 45 | 26% | 76 | 43% | 17%; (8%, 27%) a
Bio-naïve⸸ | 30/84 | 36% | 38/79 | 48%
Prior biologic failure | 15/88 | 17% | 35/91 | 38%
Maintenance of Clinical Remission at Week 44 in subjects who achieved clinical remission 8 weeks after induction | 18/50 | 36% | 27/41 | 66% | 31%; (12%, 50%) b
Bio-naïve⸸ | 12/27 | 44% | 14/20 | 70%
Prior biologic failure | 6/23 | 26% | 12/18 | 67%
⸸ An additional 3 subjects on placebo and 6 subjects on ustekinumab had been exposed to, but had not failed, biologics.
* The placebo group consisted of subjects who were in response to ustekinumab and were randomized to receive placebo at the start of maintenance therapy.
** Clinical remission was defined as Mayo stool frequency subscore of 0 or 1, Mayo rectal bleeding subscore of 0, and Mayo endoscopy subscore of 0 or 1 (modified so that 1 does not include friability).
† Clinical response was defined as a decrease from baseline in the modified Mayo score by ≥30% and ≥2 points, with either a decrease from baseline in the rectal bleeding subscore ≥1 or a rectal bleeding subscore of 0 or 1.
§ Endoscopic improvement was defined as Mayo endoscopy subscore of 0 or 1 (modified so that 1 does not include friability).
‡ Corticosteroid-free clinical remission was defined as subjects in clinical remission and not receiving corticosteroids at Week 44.
a p =<0.001
b p=0.004

Other Endpoints

Week 16 Responders to Ustekinumab Induction

Subjects who were not in clinical response 8 weeks after induction with ustekinumab in UC-1 were not included in the primary efficacy analyses for trial UC-2; however, these subjects were eligible to receive a 90 mg subcutaneous injection of ustekinumab at Week 8. Of these subjects, 55/101 (54%) achieved clinical response eight weeks later (Week 16) and received ustekinumab 90 mg subcutaneously every 8 weeks during the UC-2 trial. At Week 44, there were 97/157 (62%) subjects who maintained clinical response and there were 51/157 (32%) who achieved clinical remission.

Histologic-Endoscopic Mucosal Improvement at Week 44

The proportion of subjects achieving histologic-endoscopic mucosal improvement during maintenance treatment in UC-2 was 75/172 (44%) among subjects on ustekinumab and 40/172 (23%) in subjects on placebo at Week 44. The relationship of histologic-endoscopic mucosal improvement, as defined in UC-2, at Week 44 to progression of disease or long-term outcomes was not evaluated in UC-2.

Endoscopic Normalization

Normalization of endoscopic appearance of the mucosa was defined as a Mayo endoscopic subscore of 0. At Week 8 in UC-1, endoscopic normalization was achieved in 25/322 (8%) of subjects treated with ustekinumab and 12/319 (4%) of subjects in the placebo group. At Week 44 of UC-2, endoscopic normalization was achieved in 51/176 (29%) of subjects treated with ustekinumab and in 32/175 (18%) of subjects in placebo group.

15 REFERENCES

1. Surveillance, Epidemiology, and End Results (SEER) Program (www.seer.cancer.gov) SEER*Stat Database: Incidence - SEER 6.6.2 Regs Research Data, Nov 2009 Sub (1973-2007) - Linked To County Attributes - Total U.S., 1969-2007 Counties, National Cancer Institute, DCCPS, Surveillance Research Program, Surveillance Systems Branch, released April 2010, based on the November 2009 submission.

16 HOW SUPPLIED/STORAGE AND HANDLING

Ustekinumab-aekn injection, is a sterile, preservative-free, clear and colorless to slightly yellow solution and free of visible particles for subcutaneous use. It is supplied as individually packaged, single-dose prefilled syringes or single-dose vials.

For Subcutaneous Use

Single-dose Prefilled Syringes

- 45 mg/0.5 mL NDC 51759-413-32

- 90 mg/mL NDC 51759-414-32

Each prefilled syringe is equipped with a 29-gauge fixed 1/2 inch needle equipped with a passive safety device and a needle cover. Not made with natural rubber latex.

Single-dose Vial

- 45 mg/0.5 mL NDC 51759-413-13

For Intravenous Infusion

Single-dose Vial

- 130 mg/26 mL (5 mg/mL) NDC 51759-415-13

Storage and Stability

Store Ustekinumab-aekn vials and prefilled syringes refrigerated between 36°F to 46°F (2°C to 8°C). Store Ustekinumab-aekn vials upright. Keep the product in the original carton to protect from light until the time of use. Do not freeze. Do not shake.

If needed, individual prefilled syringes may be stored at room temperature up to 86°F (30°C) for a maximum single period of up to 30 days in the original carton to protect from light. Record the date when the prefilled syringe is first removed from the refrigerator on the carton in the space provided. Once a syringe has been stored at room temperature, do not return to the refrigerator. Discard the syringe if not used within 30 days at room temperature storage. Do not use Ustekinumab-aekn after the expiration date on the carton or on the prefilled syringe.

If needed, Ustekinumab-aekn 130 mg vials may be stored at room temperature up to 86°F (30°C) for a maximum single period of up to 7 days, in the original carton to protect from light. Once a vial has been stored at room temperature, do not return to the refrigerator. Discard the vial if not used within 7 days at room temperature storage. Do not use Ustekinumab-aekn after the expiration date on the carton or on the vial.

17 PATIENT COUNSELING INFORMATION

Advise the patient and/or caregiver to read the FDA-approved patient labeling (Medication Guide and Instructions for Use).

Infections
Inform patients that Ustekinumab-aekn may lower the ability of their immune system to fight infections and to contact their healthcare provider immediately if they develop any signs or symptoms of infection [see Warnings and Precautions (5.1)].

Malignancies
Inform patients of the risk of developing malignancies while receiving Ustekinumab-aekn [see Warnings and Precautions (5.4)].

Serious Hypersensitivity and Reactions
Advise patients to seek immediate medical attention if they experience any signs or symptoms of serious hypersensitivity reactions and discontinue Ustekinumab-aekn [see Warnings and Precautions (5.5)].

Posterior Reversible Encephalopathy Syndrome (PRES)

Inform patients to immediately contact their healthcare provider if they experience signs and symptoms of PRES (which may include headache, seizures, confusion, or visual disturbances) [see Warnings and Precautions (5.6)].

Immunizations
Inform patients that Ustekinumab-aekn can interfere with the usual response to immunizations and that they should avoid live vaccines [see Warnings and Precautions (5.7)].

Administration
Instruct patients to follow sharps disposal recommendations, as described in the Instructions for Use.

Brands listed are the trademarks of their respective owners.

Manufactured By:
Alvotech USA Inc.
Leesburg, VA 20175
U.S. License No. 2225

Product of Iceland

Marketed By:
Teva Pharmaceuticals
Parsippany, NJ 07054

MEDICATION GUIDE
Ustekinumab-aekn(u-ste-KIN-u-mab aekn)
injection, for subcutaneous or intravenous use

What is the most important information I should know about Ustekinumab-aekn?
Ustekinumab-aekn is a medicine that affects your immune system. Ustekinumab-aekn can increase your risk of having serious side
effects, including:

Serious infections.Ustekinumab-aeknmay lower the ability of your immune system to fight infections and may increase your risk of infections. Some people have serious infections during treatment with ustekinumab products, including tuberculosis (TB), and infections caused by bacteria, fungi, or viruses. Some people have to be hospitalized for treatment of their infection.

- Your healthcare provider should check you for TB before starting Ustekinumab-aekn.
- If your healthcare provider feels that you are at risk for TB, you may be treated with medicine for TB before you begin treatment with Ustekinumab-aekn and during treatment with Ustekinumab-aekn.
- Your healthcare provider should watch you closely for signs and symptoms of TB while you are being treated with Ustekinumab-aekn.

You should not start Ustekinumab-aekn if you have any kind of infection unless your healthcare provider says it is okay.

Before startingUstekinumab-aekn, tell your healthcare provider if you:

- think you have an infection or have symptoms of an infection such as:

- fever, sweat, or chills
- muscle aches
- cough
- shortness of breath
- blood in phlegm
- weight loss
- warm, red, or painful skin or sores on your body
- diarrhea or stomach pain
- burning when you urinate or urinate more often than normal
- feel very tired

- are being treated for an infection or have any open cuts.
- get a lot of infections or have infections that keep coming back.
- have TB, or have been in close contact with someone with TB.

After starting Ustekinumab-aekn, call your healthcare provider right away if you have any symptoms of an infection (see above). These may be signs of infections such as chest infections, or skin infections or shingles that could have serious complications. Ustekinumab-aekn can make you more likely to get infections or make an infection that you have worse.

People who have a genetic problem where the body does not make any of the proteins interleukin 12 (IL-12) and interleukin 23 (IL-23) are at a higher risk for certain serious infections. These infections can spread throughout the body and cause death. People who take Ustekinumab-aekn may also be more likely to get these infections.

Cancers. Ustekinumab-aekn may decrease the activity of your immune system and increase your risk for certain types of cancers. Tell your healthcare provider if you have ever had any type of cancer. Some people who are receiving ustekinumab products and have risk factors for skin cancer have developed certain types of skin cancers. During your treatment with Ustekinumab-aekn, tell your healthcare provider if you develop any new skin growths.

What is Ustekinumab-aekn?

Ustekinumab-aekn is a prescription medicine used to treat:

- adults and children 6 years of age and older with moderate to severe plaque psoriasis who may benefit from taking injections or pills (systemic therapy) or phototherapy (treatment using ultraviolet light alone or with pills).
- adults and children 6 years of age and older with active psoriatic arthritis.
- adults with moderately to severely active Crohn’s disease.
- adults with moderately to severely active ulcerative colitis.

It is not known if Ustekinumab-aekn is safe and effective in children with Crohn’s disease or ulcerative colitis or in children less than 6 years of age with plaque psoriasis or psoriatic arthritis.

Who should not use Ustekinumab-aekn?
Do not use Ustekinumab-aekn if you are allergic to ustekinumab products or any of the ingredients in Ustekinumab-aekn. See the end of this Medication Guide for a complete list of ingredients in Ustekinumab-aekn.

Before you use or receive Ustekinumab-aekn, tell your healthcare provider about all of your medical conditions, including if you:

- have any of the conditions or symptoms listed in the section “What is the most important information I should know about Ustekinumab-aekn?”
- ever had an allergic reaction to ustekinumab products. Ask your healthcare provider if you are not sure.
- have recently received or are scheduled to receive an immunization (vaccine). People who are being treated with Ustekinumab-aekn should avoid receiving live vaccines. Tell your healthcare provider if anyone in your house needs a live vaccine. The viruses used in some types of live vaccines can spread to people with a weakened immune system, and can cause serious problems. You should avoid receiving the BCG vaccine during the one year before receiving Ustekinumab-aekn or one year after you stop receiving Ustekinumab-aekn.

- have any new or changing lesions within psoriasis areas or on normal skin.
- are receiving or have received allergy shots, especially for serious allergic reactions. Allergy shots may not work as well for you during treatment with Ustekinumab-aekn. Ustekinumab-aekn may also increase your risk of having an allergic reaction to an allergy shot.
- receive or have received phototherapy for your psoriasis.
- are pregnant or plan to become pregnant. It is not known if Ustekinumab-aekn can harm your unborn baby. You and your healthcare provider should decide if you will receive Ustekinumab-aekn.
- are breastfeeding or plan to breastfeed. Ustekinumab-aekn can pass into your breast milk.
- Talk to your healthcare provider about the best way to feed your baby if you receive Ustekinumab-aekn.

Tell your healthcare provider about all the medicines you take, including prescription and over-the-counter medicines, vitamins, and herbal supplements.

Know the medicines you take. Keep a list of them to show your healthcare provider and pharmacist when you get a new medicine.

How should I use Ustekinumab-aekn?

- Use Ustekinumab-aekn exactly as the healthcare provider tells you to. The healthcare provider will determine the right dose of Ustekinumab-aekn, the amount for each injection, and how often it should be given. Be sure to keep all scheduled follow-up appointments.
- Adults with Crohn’s disease and ulcerative colitis will receive the first dose of Ustekinumab-aekn through a vein in the arm (intravenous infusion) in a healthcare facility by a healthcare provider. It takes at least 1 hour to receive the full dose of medicine. Ustekinumab-aekn will then be received as an injection under the skin (subcutaneous injection) 8 weeks after the first dose of Ustekinumab-aekn, as described below.
- Adults and children 6 years of age and older with plaque psoriasis or psoriatic arthritis will receive Ustekinumab-aekn as an injection under the skin as described below.
- Injecting Ustekinumab-aekn under the skin
  - Ustekinumab-aekn is intended for use under the guidance and supervision of a healthcare provider.
  - In children, it is recommended that Ustekinumab-aekn be administered by a healthcare provider. If a healthcare provider decides that you or a caregiver may give the injections of Ustekinumab-aekn at home, you or a caregiver should receive training on the right way to prepare and inject Ustekinumab-aekn.
  - Do not try to inject Ustekinumab-aeknuntil you have been shown how to inject Ustekinumab-aekn by a healthcare provider.
  - Ustekinumab-aekn can be injected under the skin in the upper arms, buttocks, upper legs (thighs) or stomach area (abdomen).
  - Do not give an injection in an area of the skin that is tender, bruised, red or hard.
  - Use a different injection site each time you use Ustekinumab-aekn.
- If you inject too much Ustekinumab-aekn, call the healthcare provider or Poison Help line at 1-800-222-1222, or go to the nearest emergency room right away.

Read the detailed Instructions for Use at the end of this Medication Guide for instructions about how to prepare and inject a dose of Ustekinumab-aekn, and how to properly throw away (dispose of) used needles, syringes and vials. The syringe, needle and vial must never be re-used. After the rubber stopper is punctured, Ustekinumab-aekn can become contaminated by harmful bacteria which could cause an infection if re-used. Therefore, throw away any unused portion of Ustekinumab-aekn.

What should I avoid while using Ustekinumab-aekn?
You should avoid receiving a live vaccine during treatment with Ustekinumab-aekn. See "Before you use or receive Ustekinumab-aekn, tell your healthcare provider about all of your medical conditions, including if you:"

What are the possible side effects of Ustekinumab-aekn?

Ustekinumab-aekn may cause serious side effects, including:

- See"What is the most important information I should know about Ustekinumab-aekn?"
- Serious allergic reactions.Serious allergic reactions can occur with Ustekinumab-aekn. Stop using Ustekinumab-aekn and get medical help right away if you get any of the following symptoms of a serious allergic reaction:

- feeling faint
- swelling of your face, eyelids, tongue, or throat
- chest discomfort
- trouble breathing
- skin rash

- Posterior Reversible Encephalopathy Syndrome (PRES).PRES is a rare condition that affects the brain and can cause death. Tell your healthcare provider right away if you get any symptoms of PRES during treatment with Ustekinumab-aekn, including:
  - headache
  - seizures
  - confusion
  - vision problems

- Lung inflammation.Cases of lung inflammation have happened in some people who receive ustekinumab products and may be serious. These lung problems may need to be treated in a hospital. Tell your healthcare provider right away if you develop shortness of breath or a cough that doesn't go away during treatment with Ustekinumab-aekn.

The most common side effects of Ustekinumab-aekn include:

- nasal congestion, sore throat, and runny nose
- upper respiratory infections
- fever
- headache
- tiredness
- itching
- nausea and vomiting
- influenza

- redness at the injection site
- vaginal yeast infections

- urinary tract infections
- sinus infection
- bronchitis
- diarrhea

- stomach pain
- joint pain

These are not all of the possible side effects of Ustekinumab-aekn. Call your doctor for medical advice about side effects. You may report side effects to FDA at 1-800-FDA-1088.
You may also report side effects to Teva Pharmaceuticals at 1-888-483-8279.

How should I store Ustekinumab-aekn?

- Store Ustekinumab-aekn vials and prefilled syringes in a refrigerator between 36°F to 46°F (2°C to 8°C).
- Store Ustekinumab-aekn vials standing up straight (upright).
- Store Ustekinumab-aekn in the original carton to protect it from light until time to use it.
- Do not freeze Ustekinumab-aekn.
- Do not shake Ustekinumab-aekn.
- If needed, individual Ustekinumab-aekn prefilled syringes may also be stored at room temperature up to 86°F (30°C) for a maximum single period of up to 30 days in the original carton to protect from light.
- Record the date when the prefilled syringe is first removed from the refrigerator on the carton in the space provided.
- After a prefilled syringe has been stored at room temperature, it should not be returned to the refrigerator.
- Throw away (discard) the prefilled syringe if not used within 30 days at room temperature storage. Do not use Ustekinumab-aekn after the expiration date on the carton or on the prefilled syringe.

Keep Ustekinumab-aekn and all medicines out of the reach of children.

General information about the safe and effective use of Ustekinumab-aekn.
Medicines are sometimes prescribed for purposes other than those listed in a Medication Guide. Do not use Ustekinumab-aekn for a condition for which it was not prescribed. Do not give Ustekinumab-aekn to other people, even if they have the same symptoms that you have. It may harm them. You can ask your pharmacist or healthcare provider for information about Ustekinumab-aekn that was written for health professionals.

What are the ingredients in Ustekinumab-aekn?
Active ingredient: ustekinumab-aekn

Inactive ingredients: Single-dose prefilled syringe and single-dose vial for subcutaneous use contains histidine, L-histidine monohydrochloride monohydrate, polysorbate 80, sucrose and water for injection. Single-dose vial for intravenous infusion contains edetate disodium, histidine, L-histidine monohydrochloride monohydrate, methionine, polysorbate 80, sucrose and water for injection.

Manufactured By: Alvotech USA Inc., Leesburg, VA 20175
U.S. License No. 2225
Product of Iceland
Marketed By: Teva Pharmaceuticals, Parsippany, NJ 07054
For more information call 1-888-483-8279.

This Medication Guide has been approved by the U.S. Food and Drug Administration Revised: 12/2025

INSTRUCTIONS FOR USE
Ustekinumab-aekn (u-ste-KIN-u-mab aekn) injection,

for subcutaneous use

This Instructions for Use contains information on how to inject Ustekinumab-aekn using a prefilled syringe.

Read this Instructions for Use before you start using Ustekinumab-aekn. A healthcare provider should show you how to prepare and give an injection of Ustekinumab-aekn the right way.

If you cannot give the injection:

- ask your healthcare provider to help you, or
- ask someone who has been trained by a healthcare provider to give your injections.

Do not try to inject Ustekinumab-aekn yourself until you have been shown how to inject Ustekinumab-aekn by a healthcare provider.

Important Information You Need to Know Before Injecting Ustekinumab-aekn

- For subcutaneous use only (inject directly under the skin).
- Before you start, check the carton to make sure that it is the right dose. You will have either 45 mg or 90 mg as prescribed by the healthcare provider.
  - If the dose is 45 mg, you will receive one 45 mg prefilled syringe.
  - If the dose is 90 mg, you will receive either one 90 mg prefilled syringe or two 45 mg prefilled syringes. If you receive two 45 mg prefilled syringes for a 90 mg dose, you will need to give two injections, one right after the other.
- Check the expiration date on the prefilled syringe and carton. If the expiration date has passed or if the prefilled syringe has been kept at room temperature up to 86°F (30°C for longer than a maximum single period of 30 days or if the prefilled syringe has been stored above 86°F (30°C), do not use it. If the expiration date has passed or if the prefilled syringe has been stored above 86°F a(30°C), or at room temperature for longer than 30 days, call the healthcare provider or pharmacist, or call 1- 888-483-8279 for help.
- Make sure the syringe is not damaged.
- Check the prefilled syringe for any particles or discoloration. The liquid in the prefilled syringe should look clear and colorless to slightly yellow solution and should not have any particles.
- Do not use if it is frozen, discolored, cloudy, or has large particles. Get a new prefilled syringe
- Do not shake the prefilled syringe at any time. Shaking the prefilled syringe may damage Ustekinumab-aekn medicine. If the prefilled syringe has been shaken, do not use it. Get a new prefilled syringe.
- To reduce the risk of accidental needle sticks, each prefilled syringe has a needle guard that is automatically activated to cover the needle after you have given the injection. Do not pull back on the plunger at any time.

Storing Ustekinumab-aekn prefilled syringes

- Store Ustekinumab-aekn prefilled syringes in the refrigerator between 36°F to 46°F (2°C to 8°C).
- Store Ustekinumab-aekn prefilled syringes in the original carton to protect it from light until time to use it.
- Do not freeze Ustekinumab-aekn prefilled syringes.
- Do not shake Ustekinumab-aekn.
- If needed, individual prefilled syringes may be stored at room temperature up to 86°F(30°C) for a maximum single period of up to 30 days in the original carton to protect from light.
- Record the date when the prefilled syringe is first removed from the refrigerator on the carton in the space provided.
- After a prefilled syringe has been stored at room temperature, do not return it to the refrigerator.
- Throw away (discard) the prefilled syringe if not used within 30 days at room temperature storage. Do not use Ustekinumab-aekn after the expiration date on the carton or on the prefilled syringe.

Keep Ustekinumab-aekn and all medicines out of the reach of children.

Preparing to inject Ustekinumab-aekn

Gather the supplies you will need to prepare and to give the injection. (See Figure B)

- You will need:
  - antiseptic wipes
  - cotton balls or gauze pads
  - adhesive bandage
  - your prescribed dose of Ustekinumab-aekn (See Figure A)
  - FDA-cleared sharps disposal container. See"Step 4: Disposing of the used prefilled syringe."

Step 1: Preparing the Injection

- Choose a well-lit, clean, flat work surface.
- Wash your hands well with soap and warm water.
- Hold the prefilled syringe with the covered needle pointing upward.

Step 2: Preparing the injection site

- Choose an injection site around the stomach area (abdomen), buttocks, or upper legs (thighs). If a caregiver is giving the injection, the outer area of the upper arms may also be used. (See Figure C)
- Use a different injection site for each injection. Do not give an injection in an area of the skin that is tender,bruised, red or hard.
- Clean the skin with an antiseptic wipe where you plan to give the injection.
- Do not touch this area again before giving the injection. Let the skin dry before injecting.
- Do not fan or blow on the clean area.
- Do not inject through clothes.

Step 3: Injecting Ustekinumab-aekn

- Remove the needle cover when you are ready to inject Ustekinumab-aekn.
- Do not touch the plunger or plunger head while removing the needle cover.
- Hold the body of the prefilled syringe with one hand, and pull the needle cover straight off. (See Figure D)
- Put the needle cover in the trash. Do not recap.
- You may also see a drop of liquid at the end of the needle. This is normal.
- Do not touch the needle or let it touch anything.
- Do not use the prefilled syringe if it is dropped without the needle cover in place.

- Hold the body of the prefilled syringe in one hand between the thumb and index fingers.(See Figure E)
- Do not pull back on the plunger at any time.

- Use the other hand to gently pinch the cleaned area of skin. Hold firmly.
- Use a quick, dart-like motion to insert the needle into the pinched skin at about a 45-degree angle. (See Figure F)

- Inject all of the liquid by using your thumb to push in the plunger until the plunger head is completely between the needle guard activation clips. (See Figure G)

- When the plunger is pushed as far as it will go, keep pressure on the plunger head. Take the needle out of the skin and then let go of the skin.
- Slowly take your thumb off the plunger head. This will let the empty syringe move up until the entire needle is covered by the needle guard. (See Figure H)

- When the needle is pulled out of the skin, there may be a little bleeding at the injection site. This is normal.
- You can press a cotton ball or gauze pad on the skin of the injection site, if needed (See Figure I). Do not rub the injection site.
- Cover the injection site with a small adhesive bandage, if necessary.

If the dose is 90 mg, you will receive either one 90 mg prefilled syringe or two 45 mg prefilled syringes. If you receive two 45 mg prefilled syringes for a 90 mg dose, you will need to give a second injection right after the first. Repeat Steps 1 to 3 for the second injection using a new syringe. Choose a different site for the second
injection.

Step 4: Disposing of the syringes

- Put the syringe in a FDA-cleared sharps disposal container right away after use (See Figure J). Do not throw away (dispose of) syringes in your household trash.

- If you do not have a FDA-cleared sharps disposal container, you may use a household container that is:
  - made of heavy-duty plastic,
  - can be closed with a tight-fitting, puncture-resistant lid, without sharps being able to come out,
  - upright and stable during use,
  - leak-resistant,
  - and properly labeled to warn of hazardous waste inside the container.
- When your sharps disposal container is almost full, you will need to follow your community guidelines for the right way to dispose of your sharps disposal container. There may be local or state laws about how to throw away syringes and needles. For more information about safe sharps disposal, and for specific information about sharps disposal in the state that you live in, go to the FDA's website at: http://www.fda.gov/safesharpsdisposal.
- Do not dispose of your sharps disposal container in your household trash unless your community guidelines permit this.
- Do not recycle your sharps disposal container.
- If you have any questions, talk to your healthcare provider or pharmacist.

Manufactured By:
Alvotech USA Inc.
Leesburg, VA 20175

U.S. License No. 2225

Product of Iceland

Marketed By:
Teva Pharmaceuticals
Parsippany, NJ 07054

For additional information, call Teva Pharmaceuticals at 1-888-483-8279.

This Instructions for Use has been approved by the U.S. Food and Drug Administration.

Revised: 12/2025

INSTRUCTIONS FOR USE

Ustekinumab-aekn (u-ste-KIN-u-mab aekn)

injection, for subcutaneous use

This Instructions for Use contains information on how to inject Ustekinumab-aekn using vial.

Read this Instructions for Use before you start using Ustekinumab-aekn. A healthcare provider should show you how to prepare, measure the dose and give an injection of Ustekinumab-aekn the right way.

If you cannot give the injection:

- ask your healthcare provider to help you, or
- ask someone who has been trained by a healthcare provider to give the injections.

Do not try to inject Ustekinumab-aekn until you have been shown how to inject Ustekinumab-aekn by a healthcare provider.

Important Information You Need to Know Before Injecting Ustekinumab-aekn:

- Before you start, check the carton to make sure that it is the right dose. You will have either 45 mg or 90 mg as prescribed by the healthcare provider.
  - If the dose is 45 mg or less you will receive one 45 mg vial.
  - If the dose is 90 mg, you will receive two 45 mg vials and you will need to give two injections, one right after the other.
- Check the expiration date on the vial and carton. If the expiration date has passed, do not use it. If the expiration date has passed, call the healthcare professional or pharmacist, or call Teva Pharmaceuticals at 1-888-483-8279 for help.
- Check the vial for any particles or discoloration. The liquid in the vial should look clear and colorless to slightly yellow and without visible particles.
- Do not use if it is frozen, discolored, cloudy or has large particles. Get a new vial.
- Do not shake the vial at any time. Shaking the vial may damage the Ustekinumab-aekn medicine. If the vial has been shaken, do not use it. Get a new vial.
- Do not use a Ustekinumab-aekn vial more than one time, even if there is medicine left in the vial. After the rubber stopper is punctured, Ustekinumab-aekn can become contaminated by harmful bacteria which could cause an infection if re-used. Therefore, throw away any unused Ustekinumab-aekn after you give the injection.
- Safely throw away (dispose of) Ustekinumab-aekn vials, needles and syringes after use. See "Step 6: Disposing of needles, syringes, and vials."
- Do not re-use syringes or needles.
- To avoid needle-stick injuries, do not recap needles.

Storing Ustekinumab-aekn Vials

- Store Ustekinumab-aekn in a refrigerator between 36°F to 46°F (2°C to 8°C).
- Store Ustekinumab-aekn standing up straight (upright).
- Store Ustekinumab-aekn in the original carton to protect it from light until time to use it.
- Do not freeze Ustekinumab-aekn vials.
- Do not shake Ustekinumab-aekn vials.

Keep Ustekinumab-aekn and all medicines out of the reach of children.

Gather the supplies you will need to prepare Ustekinumab-aekn and to give your injection. (See Figure A)

You will need:

- a syringe with the needle attached, you will need a prescription from a healthcare provider to get syringes with the needles attached from a pharmacy.
- antiseptic wipes
- cotton balls or gauze pads
- adhesive bandage
- your prescribed dose of Ustekinumab-aekn
- FDA-cleared sharps disposal container. See “Step 6: Disposing of the needles and syringes.”

Step 1: Preparing the injection.

- Choose a well-lit, clean, flat work surface.
- Wash your hands well with soap and warm water.

Step 2: Preparing your injection site.

- Choose an injection site around your stomach area (abdomen), buttocks, and upper legs (thighs).
- If a caregiver is giving you the injection, the outer area of the upper arms may also be used. (See Figure B)
- Use a different injection site for each injection. Do not give an injection in an area of the skin that is tender, bruised, red or hard.
- Clean the skin with an antiseptic wipe where you plan to give the injection.
- Do not touch this area again before giving the injection. Let the skin dry before injecting.
- Do not fan or blow on the clean area.

*Areas in yellow are recommended injection sites

Step 3: Preparing the vial.

- Remove the cap from the top of the vial. Throw away the cap but do not remove the rubber stopper. (See Figure C)

- Clean the rubber stopper with an antiseptic wipe. (See Figure D)

- Do not touch the rubber stopper after you clean it.
- Put the vial on a flat surface.

Step 4: Preparing the syringe

- Pick up the syringe with the needle attached.
- Remove the cap that covers the needle. (See Figure E)
- Throw the needle cap away. Do not touch the needle or allow the needle to touch anything.

- Carefully pull back on the plunger to the line that matches the dose prescribed by the healthcare provider.
- Hold the vial between your thumb and index (pointer) finger.
- Use your other hand to push the syringe needle through the center of the rubber stopper. (See Figure F)

- Push down on the plunger until all of the air has gone from the syringe into the vial.
- Turn the vial and the syringe upside down. (See Figure G)
- Hold the Ustekinumab-aekn vial with one hand.
- It is important that the needle is always in the liquid in order to prevent air bubbles forming in the syringe.
- Pull back on the syringe plunger with your other hand.
- Fill the syringe until the black tip of the plunger lines up with the mark that matches the prescribed dose.

- Do not remove the needle from the vial. Hold the syringe with the needle pointing up to see if it has any air bubbles inside.
- If there are air bubbles, gently tap the side of the syringe until the air bubbles rise to the top. (See Figure H)
- Slowly press the plunger up until all of the air bubbles are out of the syringe (but none of the liquid is out).
- Remove the syringe from the vial. Do not lay the syringe down or allow the needle to touch anything.

Step 5: Injecting Ustekinumab-aekn.

- Hold the barrel of the syringe in one hand, between the thumb and index fingers.
- Do not pull back on the plunger at any time.
- Use the other hand to gently pinch the cleaned area of skin. Hold firmly.
- Use a quick, dart-like motion to insert the needle into the pinched skin at about a 45-degree angle. (See Figure I)

- Push the plunger with your thumb as far as it will go to inject all of the liquid. Push it slowly and evenly, keeping the skin gently pinched.
- When the syringe is empty, pull the needle out of your skin and let go of the skin. (See Figure J)

- When the needle is pulled out of the skin, there may be a little bleeding at the injection site. This is normal. You can press a cotton ball or gauze pad to the injection site if needed. Do not rub the injection site. You may cover the injection site with a small adhesive bandage, if necessary.
  If the dose is 90 mg, you will receive two 45 mg vials and you will need to give a second injection right after the first. Repeat Steps 1 to 5 for using a new syringe. Choose a different site for the second injection.

Step 6: Disposing of the needles, syringes and vials.

- Do not re-use a syringe or needle.
- To avoid needle-stick injuries, do not recap a needle.
- Put the needles and syringes in a FDA-cleared sharps disposal container right away after use. Do not throw away (dispose of) loose needles and syringes in your household trash.
- If you do not have an FDA-cleared sharps disposal container, you may use a household container that is:
  - made of heavy-duty plastic
  - can be closed with a tight-fitting, puncture-resistant lid, without sharps being able to come out
  - upright and stable during use
  - leak-resistant,
  - and properly labeled to warn of hazardous waste inside the container.
- When your sharps disposal container is almost full, you will need to follow your community guidelines for the right way to dispose of your sharps disposal container. There may be local or state laws about how to throw away syringes and needles. For more information about safe sharps disposal, and for specific information about sharps disposal in the state that you live in, go to the FDA’s website at: http://www.fda.gov/safesharpsdisposal.
- Do not dispose of your sharps disposal container in your household trash unless your community guidelines permit this. Do not recycle your sharps disposal container.
- Throw away the vial into the container where you put the syringes and needles.
- If you have any questions, talk to your healthcare provider or pharmacist.

For additional information, call Teva Pharmaceuticals at 1-888-483-8279.

Manufactured By: Alvotech USA Inc., Leesburg, VA 20175

U.S. License No. 2225

Product of Iceland

Marketed By: Teva Pharmaceuticals, Parsippany, NJ 07054

This Instructions for Use has been approved by the U.S. Food and Drug Administration. Approved: 12/2025

PACKAGE.LABEL.PRINCIPAL DISPLAY PANEL

NDC 51759-413-32

Ustekinumab-aekn

Injection

45 mg/0.5 mL

For Subcutaneous Use

ATTENTION PHARMACIST: Each patient is required
to receive the enclosed Medication Guide.

Single-Dose Prefilled Syringe
Discard Unused Portion

Contains one 45 mg/0.5 mL syringe

PACKAGE.LABEL.PRINCIPAL DISPLAY PANEL

NDC 51759-414-32

Ustekinumab-aekn

Injection

90 mg/mL

For Subcutaneous Use

ATTENTION PHARMACIST: Each patient is required
to receive the enclosed Medication Guide.

Single-Dose Prefilled Syringe
Discard Unused Portion

Contains one 90 mg/mL syringe